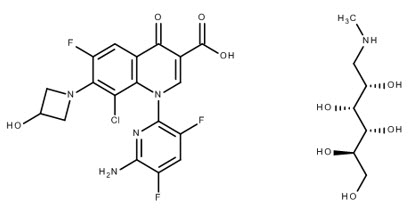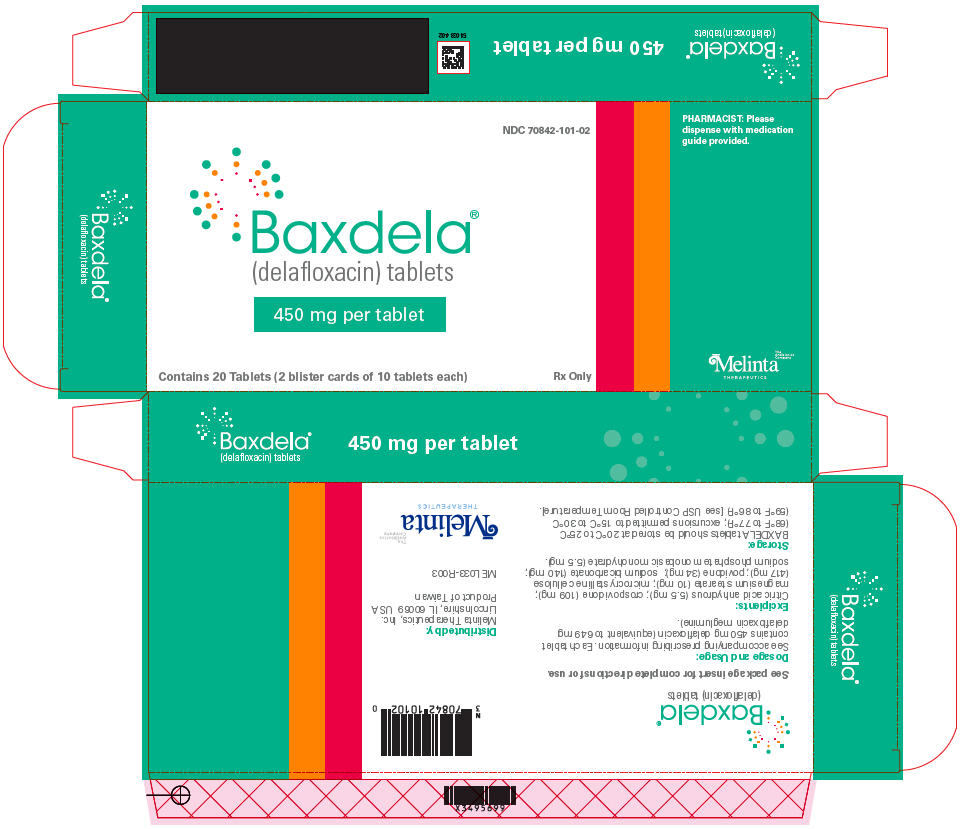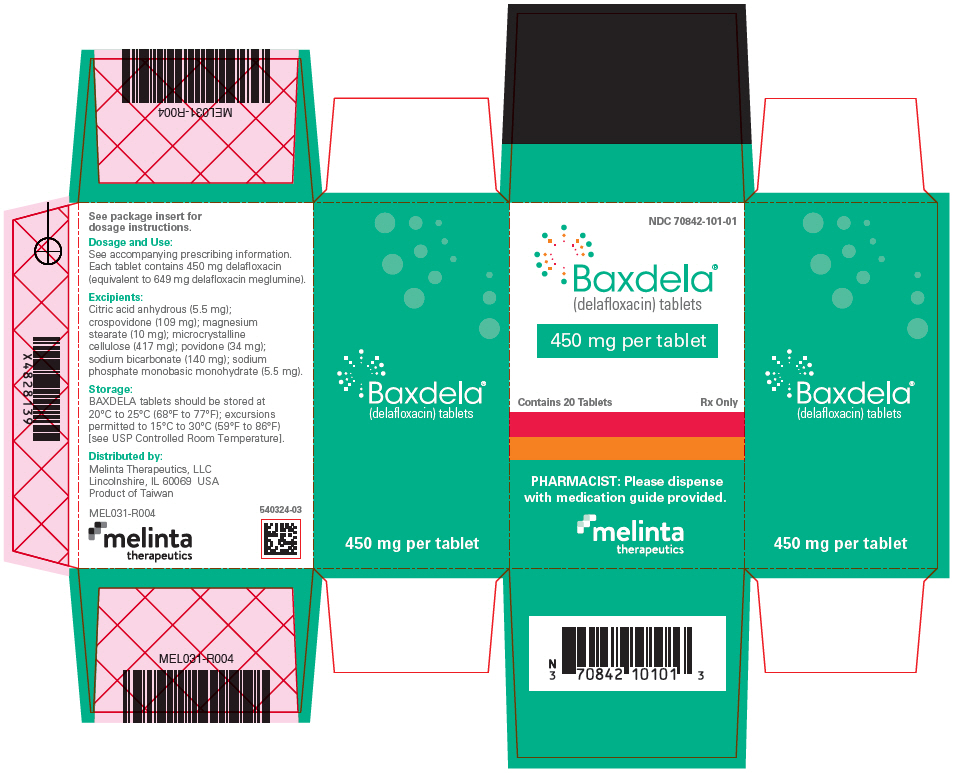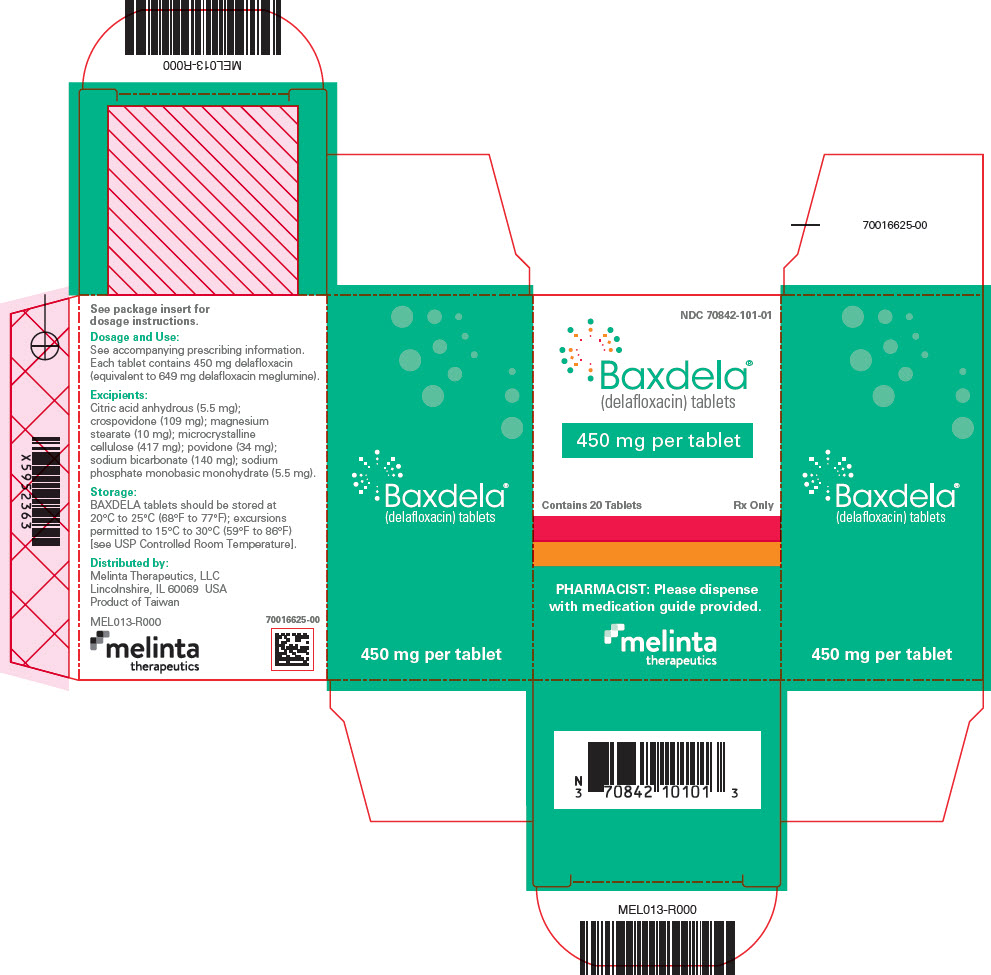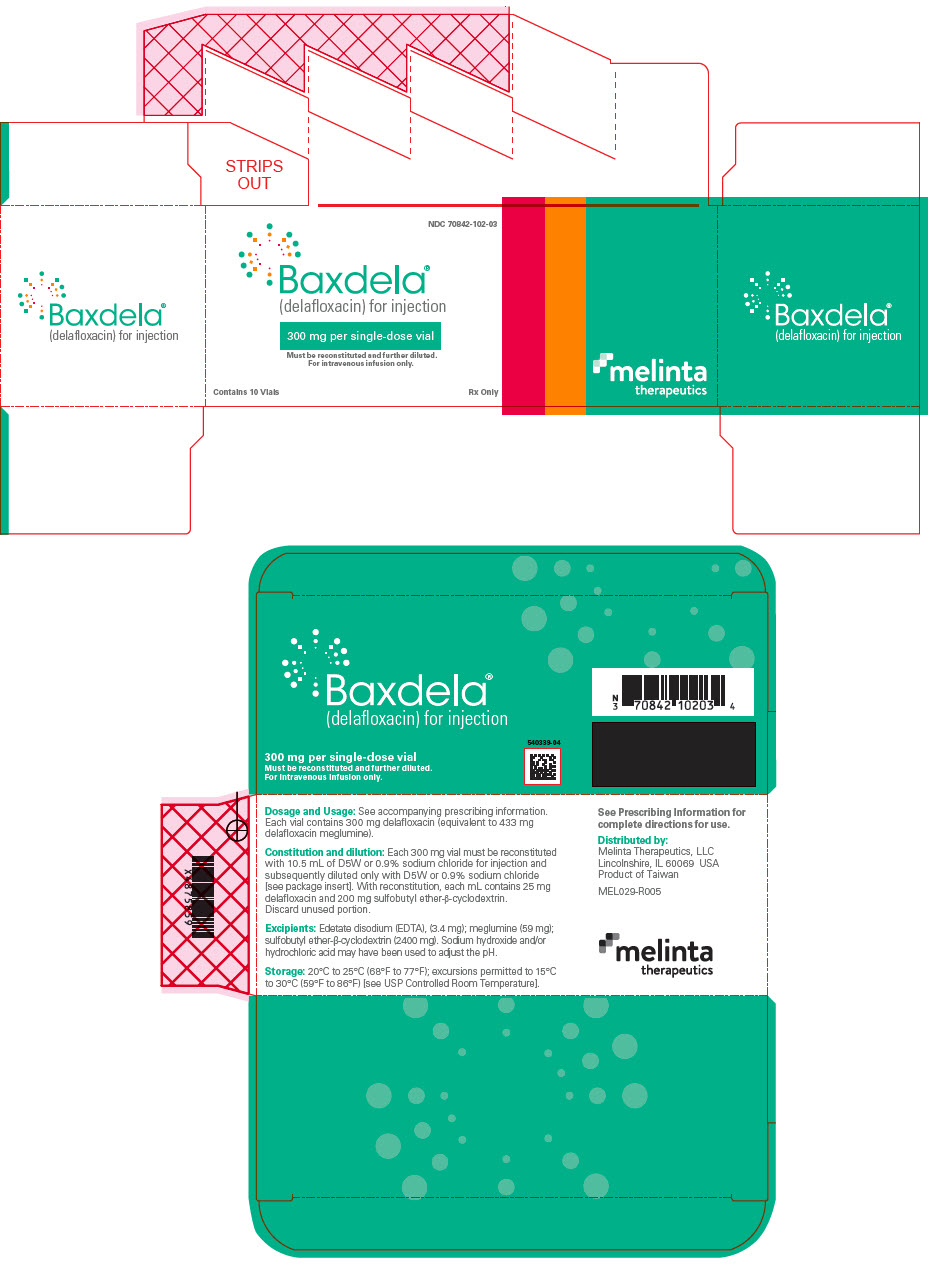 DRUG LABEL: Baxdela
NDC: 70842-101 | Form: TABLET
Manufacturer: Melinta Therapeutics, LLC
Category: prescription | Type: HUMAN PRESCRIPTION DRUG LABEL
Date: 20250801

ACTIVE INGREDIENTS: DELAFLOXACIN MEGLUMINE 450 mg/1 1
INACTIVE INGREDIENTS: MICROCRYSTALLINE CELLULOSE 417 mg/1 1; POVIDONE K30 34 mg/1 1; CROSPOVIDONE (35 .MU.M) 109 mg/1 1; SODIUM BICARBONATE 140 mg/1 1; SODIUM PHOSPHATE, MONOBASIC, MONOHYDRATE 5.5 mg/1 1; ANHYDROUS CITRIC ACID 5.5 mg/1 1; MAGNESIUM STEARATE 10 mg/1 1; WATER

HIGHLIGHTS OF PRESCRIBING INFORMATION

These highlights do not include all the information needed to use BAXDELA® safely and effectively. See full prescribing information for BAXDELA.
BAXDELA (delafloxacin) tablets, for oral use
BAXDELA (delafloxacin) for injection, for intravenous use
Initial U.S. Approval: 2017

WARNING: SERIOUS ADVERSE REACTIONS INCLUDING TENDINITIS, TENDON RUPTURE, PERIPHERAL NEUROPATHY, CENTRAL NERVOUS SYSTEM EFFECTS and EXACERBATION OF MYASTHENIA GRAVIS

See full prescribing information for complete boxed warning.

Fluoroquinolones have been associated with disabling and potentially irreversible serious adverse reactions that have occurred together (5.1), including:

- Tendinitis and tendon rupture (5.2)
- Peripheral neuropathy (5.3)
- Central nervous system effects (5.4)

Discontinue BAXDELA immediately and avoid the use of fluoroquinolones, including BAXDELA, in patients who experience any of these serious adverse reactions. (5.1)

- Fluoroquinolones may exacerbate muscle weakness in patients with myasthenia gravis. Avoid BAXDELA in patients with known history of myasthenia gravis. (5.5)

1 INDICATIONS AND USAGE

BAXDELA is a fluoroquinolone antibacterial indicated for the treatment of adults with the following infections caused by designated susceptible bacteria:

- Acute Bacterial Skin and Skin Structure Infections (ABSSSI) (1.1)
- Community-Acquired Bacterial Pneumonia (CABP) (1.2)

To reduce the development of drug-resistant bacteria and maintain the effectiveness of BAXDELA and other antibacterial drugs, BAXDELA should be used only to treat or prevent infections that are proven or strongly suspected to be caused by bacteria. (1.3)

2 DOSAGE AND ADMINISTRATION

- For ABSSSI and CABP: Administer BAXDELA for injection 300 mg by intravenous infusion over 60 minutes, every 12 hours, or a 450 mg BAXDELA tablet orally every 12 hours. (2.1, 2.2)
- Recommended duration of treatment: (2.2)
  - ABSSSI: 5 to 14 days
  - CABP: 5 to 10 days
- Dosage for patients with renal impairment is based on the estimated glomerular filtration rate (eGFR) (2.3)

Estimated Glomerular Filtration Rate (eGFR)(mL/min/1.73m^2) [Estimate of GFR based on a Modification of Diet in Renal Disease (MDRD) equation.] | Recommended Dosage Regimen for BAXDELA [For a total treatment duration of 5 to 14 days for the treatment of ABSSSI and 5 to 10 days for the treatment of CABP.]
 | Oral | Intravenous [All intravenous doses of BAXDELA are administered over 60 minutes.]
30-89 | No dosage adjustment | No dosage adjustment
15-29 | No dosage adjustment | 200 mg every 12 hours
End Stage Renal Disease (ESRD) (< 15 including hemodialysis) | Not Recommended [Not recommended due to insufficient information to provide dosing recommendations.]

3 DOSAGE FORMS AND STRENGTHS

- For Injection: 300 mg of delafloxacin (equivalent to 433 mg delafloxacin meglumine) as a lyophilized powder in a single dose vial for reconstitution and further dilution before intravenous infusion. (3)
- Oral Tablets: 450 mg delafloxacin (equivalent to 649 mg delafloxacin meglumine). (3)

4 CONTRAINDICATIONS

Known hypersensitivity to BAXDELA or other fluoroquinolones. (4, 5.6)

5 WARNINGS AND PRECAUTIONS

- Hypersensitivity Reactions: May occur after first or subsequent doses of BAXDELA. Discontinue BAXDELA at the first sign of a skin rash or any other sign of hypersensitivity. (5.6)
- Clostridium difficile-associated diarrhea: Evaluate if diarrhea occurs. (5.7)

6 ADVERSE REACTIONS

Most common adverse reactions (incidence ≥ 2%) are nausea, diarrhea, headache, transaminase elevations, and vomiting. (6.1)

To report SUSPECTED ADVERSE REACTIONS, contact Melinta Therapeutics at 1-844-633-6568 or FDA at 1-800-FDA-1088 or www.fda.gov/medwatch

8 USE IN SPECIFIC POPULATIONS

Renal Impairment: Closely monitor serum creatinine levels in patients with severe renal impairment (eGFR 15-29 mL/min/1.73 m^2) receiving intravenous delafloxacin. If serum creatinine level increases occur, consider changing to oral delafloxacin. Discontinue BAXDELA if eGFR decreases to < 15 mL/min/1.73 m^2 (8.6).

FULL PRESCRIBING INFORMATION

WARNING: SERIOUS ADVERSE REACTIONS INCLUDING TENDINITIS, TENDON RUPTURE, PERIPHERAL NEUROPATHY, CENTRAL NERVOUS SYSTEM EFFECTS and EXACERBATION OF MYASTHENIA GRAVIS

Fluoroquinolones have been associated with disabling and potentially irreversible serious adverse reactions that have occurred together (5.1), including:

- Tendinitis and tendon rupture (5.2)
- Peripheral neuropathy (5.3)
- Central nervous system effects (5.4)

Discontinue BAXDELA immediately and avoid the use of fluoroquinolones, including BAXDELA, in patients who experience any of these serious adverse reactions (5.1)

Fluoroquinolones may exacerbate muscle weakness in patients with myasthenia gravis. Avoid BAXDELA in patients with known history of myasthenia gravis. (5.5)

1 INDICATIONS AND USAGE

1.1 Acute Bacterial Skin and Skin Structure Infections

BAXDELA is indicated in adults for the treatment of acute bacterial skin and skin structure infections (ABSSSI) caused by the following susceptible microorganisms: Staphylococcus aureus (including methicillin-resistant [MRSA] and methicillin-susceptible [MSSA] isolates), Staphylococcus haemolyticus, Staphylococcus lugdunensis, Streptococcus agalactiae, Streptococcus anginosus Group (including Streptococcus anginosus, Streptococcus intermedius, and Streptococcus constellatus), Streptococcus pyogenes, Enterococcus faecalis, Escherichia coli, Enterobacter cloacae, Klebsiella pneumoniae, and Pseudomonas aeruginosa.

1.2 Community-Acquired Bacterial Pneumonia

BAXDELA is indicated in adults for the treatment of community-acquired bacterial pneumonia (CABP) caused by the following susceptible microorganisms: Streptococcus pneumoniae, Staphylococcus aureus (methicillin-susceptible [MSSA] isolates only), Klebsiella pneumoniae, Escherichia coli, Pseudomonas aeruginosa, Haemophilus influenzae, Haemophilus parainfluenzae, Chlamydia pneumoniae, Legionella pneumophila, and Mycoplasma pneumoniae.

1.3 Usage

To reduce the development of drug-resistant bacteria and maintain the effectiveness of BAXDELA and other antibacterial drugs, BAXDELA should be used only to treat or prevent infections that are proven or strongly suspected to be caused by susceptible bacteria. When culture and susceptibility information are available, they should be considered in selecting or modifying antibacterial therapy. In the absence of such data, local epidemiology and susceptibility patterns may contribute to the empiric selection of therapy.

2 DOSAGE AND ADMINISTRATION

2.1 Important Administration Instructions

BAXDELA Tablets

Administer BAXDELA at least 2 hours before or 6 hours after antacids containing magnesium, or aluminum, with sucralfate, with metal cations such as iron, or with multivitamin preparations containing zinc or iron, or with didanosine buffered tablets for oral suspension or the pediatric powder for oral solution [see Drug Interactions (7.1)].

BAXDELA Tablets can be taken with or without food [see Clinical Pharmacology (12.3)].

If patients miss a dose, they should take it as soon as possible anytime up to 8 hours prior to their next scheduled dose. If less than 8 hours remain before the next dose, wait until their next scheduled dose.

BAXDELA for Injection

Do NOT administer BAXDELA for Injection with any solution containing multivalent cations, e.g., calcium and magnesium, through the same intravenous line [see Drug Interactions (7.1)]. Do NOT co-infuse BAXDELA for Injection with other medications [see Dosage and Administration (2.4)].

2.2 Recommended Dosage Regimen

For treatment of adults with ABSSSI or CABP, the recommended dosage regimen of BAXDELA is described in Table 1 below.

Table 1 Dosage of BAXDELA in Adult ABSSSI or CABP Patients
Infection | Dosage and Route of Administration | Total Duration (days)
ABSSSI | - 300 mg of BAXDELA for Injection every 12 hours over 60 minutes by intravenous infusion Or - 300 mg of BAXDELA for Injection every 12 hours over 60 minutes by intravenous infusion, then switch to a 450 mg BAXDELA tablet orally every 12 hours at the discretion of the physician Or - 450 mg BAXDELA tablet orally every 12 hours. | 5 to 14
CABP | - 300 mg of BAXDELA for Injection every 12 hours over 60 minutes by intravenous infusion Or - 300 mg of BAXDELA for Injection every 12 hours over 60 minutes by intravenous infusion, then switch to a 450 mg BAXDELA tablet orally every 12 hours at the discretion of the physician Or - 450 mg BAXDELA tablet orally every 12 hours. | 5 to 10

2.3 Dosage in Patients with Renal Impairment

Table 2 below describes the dosage modification based on the estimated glomerular filtration rate (eGFR) that is recommended in patients with renal impairment. Dosage adjustment is required for patients with severe renal impairment (eGFR 15-29 mL/min/1.73m^2).

In patients with severe renal impairment receiving BAXDELA intravenously, closely monitor serum creatinine levels and eGFR [see Use in Specific Populations (8.7)]. If serum creatinine level increases, consider switching to BAXDELA Tablets. Discontinue BAXDELA if eGFR decreases to < 15 mL/min/1.73 m^2.

Table 2 Dosage Adjustment of BAXDELA in Patients with Renal Impairment
Estimated Glomerular Filtration Rate (eGFR) (mL/min/1.73 m^2) [As calculated using the MDRD eGFR equation as follows: eGFR (mL/min/1.73m^2) = 175 × (serum creatinine)^-1.154 × (age)^-0.203 × (0.742 if female) × (1.212 if African American).] | Recommended Dosage Regimen [For a total treatment duration of 5 to 14 days for the treatment of ABSSSI and 5 to 10 days for the treatment of CABP in adult patients.]
Estimated Glomerular Filtration Rate (eGFR) (mL/min/1.73 m^2) [As calculated using the MDRD eGFR equation as follows: eGFR (mL/min/1.73m^2) = 175 × (serum creatinine)^-1.154 × (age)^-0.203 × (0.742 if female) × (1.212 if African American).] | BAXDELA Tablets | BAXDELA for Injection [All doses of BAXDELA are administered by intravenous infusion over 60 minutes.]
30-89 | No dosage adjustment | No dosage adjustment
15-29 | No dosage adjustment | 200 mg every 12 hours Or 200 mg every 12 hours, then switch to a 450 mg BAXDELA tablet orally every 12 hours at the discretion of the physician
End Stage Renal Disease (ESRD) (< 15), including patients on hemodialysis (HD) | Not Recommended [Not recommended due to insufficient information to provide dosing recommendations.]

2.4 Preparation and Administration of BAXDELA for Injection Intravenous Solution

Reconstitution and Dilution

1. BAXDELA must be reconstituted and then further diluted under aseptic conditions. Reconstitute the powder in the BAXDELA vial using 10.5 mL of 5% Dextrose Injection (D5W) or 0.9% Sodium Chloride Injection for each 300 mg vial. Shake the vial vigorously until contents are completely dissolved. The reconstituted vial contains 300 mg per 12 mL (25 mg/mL) of BAXDELA as a clear yellow to amber colored solution.
2. The reconstituted solution must then be diluted to a total volume of 250 mL using either 0.9% Sodium Chloride or D5W to achieve a concentration of 1.2 mg/mL, prior to administration. Prepare the required dose for intravenous infusion by withdrawing the appropriate volume from the reconstituted vial per Table 3 below:
  Table 3 Preparation of BAXDELA Doses
  BAXDELA for Injection Dose | Volume of Reconstituted Solution to Withdraw
  300 mg | 12 mL
  200 mg | 8 mL
3. Aseptically transfer the required volume of BAXDELA reconstituted solution from the vial to an intravenous bag to achieve a 250 mL volume of infusion solution. Discard any unused portion of the reconstituted solution.
4. Parenteral drug products should be inspected visually for particulate matter and discoloration prior to administration, whenever solution and container permit.

Storage of the Reconstituted and Diluted Solutions

Reconstituted vials, as described above, may be stored either refrigerated at 2°C to 8°C (36°F to 46°F), or at controlled room temperature 20°C to 25°C (68°F to 77°F) for up to 24 hours. Do not freeze.

Once diluted into the intravenous bag, as described above, BAXDELA may be stored either refrigerated at 2°C to 8°C (36°F to 46°F) or at a controlled room temperature of 20°C to 25°C (68°F to 77°F) for up to 24 hours. Do not freeze.

Administration

After reconstitution and dilution, administer BAXDELA by intravenous infusion, using a total infusion time of 60 minutes [see Dosage and Administration (2.1)].

The compatibility of reconstituted BAXDELA with intravenous medications, additives, or substances other than D5W or 0.9% Sodium Chloride Injection has not been established. If a common intravenous line is being used to administer other drugs in addition to BAXDELA the line should be flushed before and after each BAXDELA infusion with 0.9% Sodium Chloride Injection or D5W.

3 DOSAGE FORMS AND STRENGTHS

BAXDELA for Injection: A sterile, lyophilized powder containing 300 mg delafloxacin (equivalent to 433 mg delafloxacin meglumine) in a single-dose vial, which must be reconstituted and further diluted prior to intravenous infusion. The lyophilized powder is a light yellow to tan cake, which may exhibit cracking and shrinkage and slight variation in texture and color.

BAXDELA Tablets: Modified capsule shaped tablets in beige to mottled beige color with RX3341 debossed on one side containing 450 mg delafloxacin (equivalent to 649 mg delafloxacin meglumine).

4 CONTRAINDICATIONS

BAXDELA is contraindicated in patients with known hypersensitivity to delafloxacin or any of the fluoroquinolone class of antibacterial drugs, or any of the components of BAXDELA [see Warnings and Precautions (5.6)].

5 WARNINGS AND PRECAUTIONS

5.1 Disabling and Potentially Irreversible Serious Adverse Reactions Including Tendinitis and Tendon Rupture, Peripheral Neuropathy and Central Nervous System Effects

Fluoroquinolones have been associated with disabling and potentially irreversible serious adverse reactions from different body systems that can occur together in the same patient. Commonly seen adverse reactions include tendinitis, tendon rupture, arthralgia, myalgia, peripheral neuropathy, and central nervous system effects (hallucinations, anxiety, depression, insomnia, severe headaches, and confusion). These reactions could occur within hours to weeks after starting a fluoroquinolone. Patients of any age or without pre-existing risk factors have experienced these adverse reactions [see Warnings and Precautions (5.2, 5.3 and 5.4)].

Discontinue BAXDELA immediately at the first signs or symptoms of any serious adverse reaction. In addition, avoid the use of fluoroquinolones, including BAXDELA, in patients who have experienced any of these serious adverse reactions associated with fluoroquinolones.

5.2 Tendinitis and Tendon Rupture

Fluoroquinolones have been associated with an increased risk of tendinitis and tendon rupture in all ages. This adverse reaction most frequently involves the Achilles tendon, and has also been reported with the rotator cuff (the shoulder), the hand, the biceps, the thumb, and other tendons. Tendinitis or tendon rupture can occur, within hours or days of starting a fluoroquinolone, or as long as several months after completion of fluoroquinolone therapy. Tendinitis and tendon rupture can occur bilaterally.

This risk of developing fluoroquinolone-associated tendinitis and tendon rupture is increased in patients over age 60 years of age, in patients taking corticosteroid drugs, and, in patients with kidney, heart, and lung transplant. Other factors that may independently increase the risk of tendon rupture include strenuous physical activity, renal failure, and previous tendon disorders such as rheumatoid arthritis. Tendinitis and tendon rupture have also occurred in patients taking fluoroquinolones who do not have the above risk factors.

Discontinue BAXDELA immediately if the patient experiences pain, swelling, inflammation or rupture of a tendon. Advise patients, at the first sign of tendon pain, swelling, or inflammation, to stop taking BAXDELA, to avoid exercise and use of the affected area, and to promptly contact their healthcare provider about changing to a non-quinolone antimicrobial drug. Avoid BAXDELA in patients who have a history of tendon disorders or have experienced tendinitis or tendon rupture.

5.3 Peripheral Neuropathy

Fluoroquinolones have been associated with an increased risk of peripheral neuropathy. Cases of sensory or sensorimotor axonal polyneuropathy affecting small and/or large axons resulting in paresthesias, hypoesthesias, dysesthesias, and weakness have been reported in patients receiving fluoroquinolones, including BAXDELA. Symptoms may occur soon after initiation of fluoroquinolones and may be irreversible in some patients [see Warnings and Precautions (5.1) and Adverse Reactions (6.1)].

Discontinue BAXDELA immediately if the patient experiences symptoms of peripheral neuropathy including pain, burning, tingling, numbness, and/or weakness or other alterations of sensation including light touch, pain, temperature, position sense, and vibratory sensation and/or motor strength in order to minimize the development of an irreversible condition. Avoid fluoroquinolones, including BAXDELA in patients who have previously experienced peripheral neuropathy [see Adverse Reactions (6.1)].

5.4 Central Nervous System Effects

Psychiatric Adverse Reactions

Fluoroquinolones, including BAXDELA, have been associated with an increased risk of psychiatric adverse reactions, including: toxic psychosis; hallucinations, or paranoia; depression, or suicidal thoughts or acts; delirium, disorientation, confusion, or disturbances in attention; anxiety, agitation, or nervousness; insomnia or nightmares; memory impairment. These adverse reactions may occur following the first dose. If these reactions occur in patients receiving BAXDELA, discontinue BAXDELA immediately and institute appropriate measures.

Central Nervous System Adverse Reactions

Fluoroquinolones have been associated with an increased risk of seizures (convulsions), increased intracranial pressure (including pseudotumor cerebri), dizziness, and tremors. As with all fluoroquinolones, use BAXDELA when the benefits of treatment exceed the risks in patients with known or suspected CNS disorders (e.g., severe cerebral arteriosclerosis, epilepsy) or in the presence of other risk factors that may predispose to seizures or lower the seizure threshold. If these reactions occur in patients receiving BAXDELA, discontinue BAXDELA immediately and institute appropriate measures.

5.5 Exacerbation of Myasthenia Gravis

Fluoroquinolones have neuromuscular blocking activity and may exacerbate muscle weakness in persons with myasthenia gravis. Post-marketing serious adverse reactions, including death and requirement for ventilator support, have been associated with fluoroquinolone use in persons with myasthenia gravis. Avoid BAXDELA in patients with known history of myasthenia gravis [see Patient Counseling Information (17)].

5.6 Hypersensitivity Reactions

Serious and occasionally fatal hypersensitivity (anaphylactic) reactions, some following the first dose, have been reported in patients receiving fluoroquinolone therapy. Some reactions were accompanied by cardiovascular collapse, loss of consciousness, tingling, pharyngeal or facial edema, dyspnea, urticaria, and itching. Hypersensitivity reactions have been reported in patients receiving BAXDELA. These reactions may occur after first or subsequent doses of BAXDELA [see Adverse Reactions (6.1)]. Discontinue BAXDELA at the first appearance of a skin rash or any other sign of hypersensitivity.

5.7 Clostridium difficile-Associated Diarrhea

Clostridium difficile-associated diarrhea (CDAD) has been reported in users of nearly all systemic antibacterial drugs, including BAXDELA, with severity ranging from mild diarrhea to fatal colitis. Treatment with antibacterial agents can alter the normal flora of the colon and may permit overgrowth of C. difficile.

C. difficile produces toxins A and B, which contribute to the development of CDAD. Hypertoxin-producing strains of C. difficile cause increased morbidity and mortality, as these infections can be refractory to antibacterial therapy and may require colectomy. CDAD must be considered in all patients who present with diarrhea following antibacterial use. Careful medical history is necessary because CDAD has been reported to occur more than 2 months after the administration of antibacterial agents.

If CDAD is suspected or confirmed, ongoing antibacterial use not directed against C. difficile should be discontinued, if possible. Appropriate measures such as fluid and electrolyte management, protein supplementation, antibacterial treatment of C. difficile, and surgical evaluation should be instituted as clinically indicated.

5.8 Risk of Aortic Aneurysm and Dissection

Epidemiologic studies report an increased risk of aortic aneurysm and dissection within two months following use of fluoroquinolones, particularly in elderly patients. The cause for the increased risk has not been identified. In patients with a known aortic aneurysm or patients who are at greater risk for aortic aneurysms, reserve BAXDELA for use only when there are no alternative antibacterial treatments available.

5.9 Development of Drug-Resistant Bacteria

Prescribing BAXDELA in the absence of a proven or strongly suspected bacterial infection or a prophylactic indication is unlikely to provide benefit to the patient and increases the risk of the development of drug-resistant bacteria.

5.10 Blood Glucose Disturbances

Fluoroquinolones have been associated with disturbances of blood glucose, including symptomatic hyperglycemia and hypoglycemia, usually in diabetic patients receiving concomitant treatment with an oral hypoglycemic agent (e.g., glyburide) or with insulin. In these patients, careful monitoring of blood glucose is recommended. Severe cases of hypoglycemia resulting in coma or death have been reported with other fluoroquinolones. If a hypoglycemic reaction occurs in a patient being treated with BAXDELA, discontinue BAXDELA and initiate appropriate therapy immediately [see Adverse Reactions (6.1)].

6 ADVERSE REACTIONS

The following serious and otherwise important adverse reactions are discussed in greater detail in other sections of labeling:

- Disabling and Potentially Irreversible Serious Adverse Reactions [see Warnings and Precautions (5.1)]
- Tendinitis and Tendon Rupture [see Warnings and Precautions (5.2)]
- Peripheral Neuropathy [see Warnings and Precautions (5.3)]
- Central Nervous System Effects [see Warnings and Precautions (5.4)]
- Hypersensitivity Reactions [see Warnings and Precautions (5.6)]
- Clostridium difficile-Associated Diarrhea [see Warnings and Precautions (5.7)]
- Blood Glucose Disturbances [see Warnings and Precautions (5.10)]

6.1 Clinical Trials Experience

Because clinical trials are conducted under widely varying conditions, adverse reaction rates observed in clinical trials of BAXDELA cannot be directly compared to rates in the clinical trials of another drug and may not reflect rates observed in practice.

Overview of the Safety Evaluation of BAXDELA

BAXDELA was evaluated in three Phase 3 multicenter, multinational, randomized, double-blind clinical trials. These trials included two trials in ABSSSI patients (Trial 1 and Trial 2) and one trial in CABP (Trial 3). A total of 1170 patients were treated with BAXDELA across all Phase 3 trials (741 patients in the two ABSSSI trials and 429 patients in the CABP trial).

Acute Bacterial Skin and Skin Structure Infections (ABSSSI)

BAXDELA was evaluated in two multicenter, multinational, randomized, double-blind, double-dummy, non-inferiority trials (Trial 1 and Trial 2) in adults with ABSSSI. In Trial 1 patients received BAXDELA 300 mg by intravenous infusion every 12 hours and in Trial 2 the patients received BAXDELA 300 mg by intravenous infusion every 12 hours for 6 doses then were switched to BAXDELA 450 mg tablets every 12 hours. The total treatment duration was 5 to 14 days. Adverse reactions were evaluated for 741 patients treated with BAXDELA and 751 patients treated with comparator antibacterial drugs. The median age of patients treated with BAXDELA was 49 years, ranging between 18 and 94 years old; 15% were age 65 years and older. Patients treated with BAXDELA were predominantly male (62%) and Caucasian (86%). The BAXDELA treated population included 44% obese patients (BMI ≥ 30 kg/m^2), 11% with diabetes, and 16% with baseline renal impairment (calculated creatinine clearance less than 90 mL/min).

Serious Adverse Reactions and Adverse Reactions Leading to Discontinuation

Serious adverse reactions occurred in 3/741 (0.4%) of patients treated with BAXDELA and in 6/751 (0.8%) of patients treated with the comparator.

BAXDELA was discontinued due to an adverse reaction in 7/741 (0.9%) patients and the comparator was discontinued due to an adverse reaction in 21/751 (2.8%) patients. The most commonly reported adverse reactions leading to study discontinuation in the BAXDELA arm included urticaria (2/741; 0.3%) and hypersensitivity (2/741; 0.3%); whereas, the most commonly reported adverse reactions leading to study discontinuation in the comparator arm included urticaria (5/751; 0.7%), rash (4/751; 0.5%), hypersensitivity and infusion site extravasation (2/751; 0.3%).

Most Common Adverse Reactions

The most common adverse reactions in patients treated with BAXDELA were nausea (8%), diarrhea (8%), headache (3%), transaminase elevations (3%), and vomiting (2%). Table 4 lists selected adverse reactions occurring in ≥ 2% of patients receiving BAXDELA in the pooled adult Phase 3 clinical trials.

Table 4 Selected Adverse Reactions Occurring in ≥ 2% of Patients Receiving BAXDELA in the Pooled Adult Phase 3 ABSSSI Clinical Trials
Adverse Reactions | BAXDELA N = 741 (%) | Vancomycin/aztreonam N = 751 (%)
Nausea | 8% | 6%
Diarrhea | 8% | 3%
Headache [The data are not an adequate basis for comparison of rates between the study drug and the active control.] | 3% | 6%
Transaminase Elevations [Pooled reports include hypertransaminasaemia, increased transaminases, and increased ALT and AST.] | 3% | 4%
Vomiting | 2% | 2%

Community-Acquired Bacterial Pneumonia

BAXDELA was evaluated in one multicenter, multinational, randomized, double-blind trial in adults with CABP (Trial 3). Patients received BAXDELA 300 mg over 60 minutes every 12 hours for a minimum of 6 doses with an option to switch to oral BAXDELA tablet 450 mg every 12 hours for the remaining doses (total of 10 to 20 doses of intravenous infusion and oral combined). Adverse reactions were evaluated for 429 patients treated with BAXDELA and 427 patients treated with moxifloxacin. The median age of patients treated with BAXDELA was 63 years, ranging between 18 and 89 years; 47.1% were 65 years of age and older and 19.6% were 75 years of age and older. Patients treated with BAXDELA were predominantly male (58.3%) and white (92.3%). The BAXDELA-treated population included patients with obesity (BMI greater than or equal to 30) (24.0%), COPD/asthma (14.2%), cardiac disease (24.2%), diabetes (16.3%), and baseline renal impairment including 36.4% with moderate renal impairment (CrCl less than 30-59 mL/min), and 4.0% with severe renal impairment (CrCl less than 29 mL/min). Overall, approximately 12.4% of patients were in PORT Risk Class II, 60.1% were in PORT Risk Class III, 26.6% were in PORT Risk Class IV, and 0.9% were in PORT Risk Class V.

Serious Adverse Reactions and Adverse Reactions Leading to Discontinuation

Serious adverse reactions occurred in 2/429 (0.5%) of patients treated with BAXDELA and in 1/427 (0.2%) of patients treated with moxifloxacin. Discontinuation due to an adverse reaction occurred in 9/429 (2.1%) patients treated with BAXDELA and in 4/427 (0.9%) treated with moxifloxacin. The most commonly reported adverse reactions leading to study drug discontinuation in the BAXDELA arm were transaminase elevations (2/429; 0.5%). The most commonly reported adverse reactions leading to study drug discontinuation in the comparator arm were infusion site reactions (1/427; 0.2%).

Most Common Adverse Reactions

The most common adverse reactions in patients treated with BAXDELA were diarrhea (5%) and transaminase elevations (5%). Table 5 lists selected adverse reactions occurring in ≥ 2% of patients receiving BAXDELA in the adult Phase 3 CABP clinical trial.

Table 5 Selected Adverse Reactions Occurring in ≥ 2% of Patients Receiving BAXDELA in the Adult Phase 3 CABP Clinical Trial
Adverse Reactions | BAXDELA N = 429 | Moxifloxacin N = 427
Diarrhea | 5% | 3%
Transaminase elevations [Includes hepatic enzyme increased, transaminases increased and alanine aminotransferase (ALT) increased.] | 5% | 3%

Adverse Reactions Occurring in Less Than 2% of Patients Receiving BAXDELA in the ABSSSI (Trials 1 and 2) and CABP (Trial 3) Clinical Trials

The following selected adverse reactions were reported in BAXDELA-treated patients at a rate of less than 2% in the ABSSSI (Trials 1 and 2) and CABP (Trial 3) clinical trials:

Blood and Lymphatic System Disorders: agranulocytosis, anemia, leukopenia, neutropenia, pancytopenia

Cardiac Disorders: sinus tachycardia, palpitations, bradycardia, ventricular extrasystoles

Ear and Labyrinth Disorders: tinnitus, vertigo, vestibular disorder

Eye Disorders: vision blurred

General disorders and administration site conditions: infusion related reactions

Gastrointestinal Disorders: abdominal pain, dyspepsia

Immune System Disorders: hypersensitivity

Infections and Infestations: Clostridium difficile infection, fungal infection, oral candidiasis, vulvovaginal candidiasis

Laboratory Investigations: blood alkaline phosphatase increased, blood creatinine increased, blood creatine phosphokinase increased

Metabolism and Nutrition Disorders: hyperglycemia, hypoglycemia

Musculoskeletal and Connective Tissue Disorders: myalgia

Nervous System Disorders: dizziness, hypoesthesia, paraesthesia, dysgeusia, presyncope, syncope

Psychiatric Disorders: agitation, anxiety, confusional state, insomnia, abnormal dreams

Renal and Urinary: renal impairment, renal failure

Skin and Subcutaneous Tissue Disorders: pruritus, urticaria, dermatitis, rash

Vascular Disorders: flushing, hypotension, hypertension

7 DRUG INTERACTIONS

7.1 Chelation Agents: Antacids, Sucralfate, Metal Cations, Multivitamins

Fluoroquinolones form chelates with alkaline earth and transition metal cations. Oral administration of BAXDELA with antacids containing aluminum or magnesium, with sucralfate, with metal cations such as iron, or with multivitamins containing iron or zinc, or with formulations containing divalent and trivalent cations such as didanosine buffered tablets for oral suspension or the pediatric powder for oral solution, may substantially interfere with the absorption of BAXDELA, resulting in systemic concentrations considerably lower than desired. Therefore, BAXDELA should be taken at least 2 hours before or 6 hours after these agents [see Dosage and Administration (2.1)].

There are no data concerning an interaction of intravenous BAXDELA with oral antacids, sucralfate, multivitamins, didanosine, or metal cations. However, BAXDELA should not be co-administered with any solution containing multivalent cations, e.g., magnesium, through the same intravenous line [see Dosage and Administration (2.1)].

8 USE IN SPECIFIC POPULATIONS

8.1 Pregnancy

Risk Summary

The limited available data with BAXDELA use in pregnant women are insufficient to inform a drug-associated risk of major birth defects and miscarriages. When delafloxacin (as the N-methyl glucamine salt) was administered orally to rats during the period of organogenesis, no malformations or fetal death were observed at up to 7 times the estimated clinical exposure based on AUC. When rats were dosed intravenously in late pregnancy and through lactation, there were no adverse effects on offspring at exposures approximating the clinical intravenous (IV) exposure based on AUC [see Data].

The background risk of major birth defects and miscarriage for the indicated population is unknown. In the U.S. general population, the estimated background risk of major birth defects and miscarriage in clinically recognized pregnancies is 2–4% and 15–20%, respectively.

Data

Animal Data

In embryo-fetal studies, oral administration of delafloxacin to pregnant rats during the period of major organogenesis resulted in maternal toxicity and reduced fetal body weights at the highest dose (1600 mg/kg/day) and fetal ossification delays at all doses. No malformations were reported up to the highest dose tested (approximately 7 times the estimated human plasma exposure based on AUC). The lowest dose, 200 mg/kg/day (approximately 2.5 times the estimated human plasma exposure based on AUC), was still toxic to the fetus, based on ossification delays. In rabbits, a species known to be extremely sensitive to maternal toxicity of antibacterial drugs, no embryo-fetal developmental toxicity was observed up to the highest dose which induced maternal toxicity (1.6 mg/kg/day, or approximately 0.01 times the estimated human plasma exposure based on AUC). In a pre-postnatal study in rats of IV administered delafloxacin, dams at the highest dose tested (120 mg/kg/day) exhibited slightly lower body weights and slightly longer gestation length than control animals. Exposure at that dose was estimated to be approximately 5 times human plasma exposure based on AUC, as determined in a separate shorter term study at an earlier stage of pregnancy. Effects on pups at that dose included increased mortality during lactation, small stature, and lower body weights, but no changes in learning and memory, sensory function, locomotor activity, developmental landmarks, or reproductive performance were reported. The No Adverse Effect Level (NOAEL) for maternal toxicity pup development in that study was 60 mg/kg/day (approximately 580 mg/day IV for a 60 kg patient, or just below the clinical IV dose).

8.2 Lactation

Risk Summary

There are no data available on the presence of delafloxacin in human milk, the effects on the breast-fed infant, or the effects on milk production. Delafloxacin is excreted in the breast milk of rats [see Data]. The developmental and health benefits of breastfeeding should be considered along with the mother's clinical need for BAXDELA and any potential adverse effects on the breast-fed child from BAXDELA or from the underlying maternal condition.

Data

After single oral dose of 20 mg/kg (approximately 194 mg for a 60 kg patient) ^14C-labeled delafloxacin on post-natal day 11, the radioactivity was transferred into the milk of lactating rats. The mean milk/plasma radioactivity concentration ratios in dams at 4 and 8 hours after dosing were 8.5 and 4.0, respectively, and essentially background by 24 hours. The rate of elimination of radioactivity was similar in milk and plasma. Absorption of radioactive drug by rat pups following nursing was observed.

8.4 Pediatric Use

Use in patients under 18 years of age is not recommended. Safety and effectiveness in pediatric patients below the age of 18 years have not been established. Pediatric studies were not conducted because risk-benefit considerations do not support the use of BAXDELA for ABSSSI in this population. Fluoroquinolones cause arthropathy in juvenile animals.

8.5 Geriatric Use

Of the 754 adult ABSSSI patients treated with BAXDELA, in Trials 1 and 2, 111/754 (15%) were 65 years of age and older. The clinical response rates at 48-72 hours for the BAXDELA-treated and comparator-treated patients were 84/111 (75.7%) and 72/101 (71.3%), respectively in ABSSSI patients aged 65 years and older compared to patients aged less than 65 years of age 529/643 (82.3%) and 538/655 (82.1%), respectively. In the safety population, of the 741 adult patients treated with BAXDELA, 18/110 (16.4%) patients aged 65 years and older and 146/631 (23.1%) patients aged less than 65 years had at least one adverse drug reaction.

Of the 431 adult CABP patients treated with BAXDELA, in Trial 3, 203/431 (47.1%) were 65 years of age and older, while 85/431 (19.7%) were 75 and over. The clinical response rates at 72-120 hours for the BAXDELA-treated and moxifloxacin-treated patients were 177/203 (87.2%) and 161/179 (89.9%), respectively in the CABP patients aged 65 years and older compared to patients aged less than 65 years old (206/228 (90.4%) and 220/249 (88.4%), respectively). In the safety population, of the 429 adult patients treated with BAXDELA, 10/84 (11.9%) patients aged 75 and older, 27/202 (13.4%) patients aged 65 years and older and 38/227 (16.7%) patients aged less than 65 years old had at least one adverse drug reaction.

Geriatric patients are at increased risk for developing severe tendon disorders including tendon rupture when being treated with a fluoroquinolone. This risk is further increased in patients receiving concomitant corticosteroid therapy. Tendinitis or tendon rupture can involve the Achilles, hand, shoulder, or other tendon sites and can occur during or after completion of therapy; cases occurring up to several months after fluoroquinolone treatment have been reported. Caution should be used when prescribing BAXDELA to elderly patients especially those on corticosteroids. Patients should be informed of this potential adverse reaction and advised to discontinue BAXDELA and contact their healthcare provider if any symptoms of tendinitis or tendon rupture occur [see Warnings and Precautions (5.1)].

Epidemiologic studies report an increased rate of aortic aneurysm and dissection within two months following use of fluoroquinolones, particularly in elderly patients [see Warnings and Precautions (5.8)].

In elderly subjects (≥ 65 years), the mean Cmax and AUC∞ of delafloxacin were about 35% higher compared with young adults, which is not considered clinically significant [see Clinical Pharmacology (12.3)].

8.6 Hepatic Impairment

No dosage adjustment is necessary for BAXDELA in patients with hepatic impairment [see Clinical Pharmacology (12.3)].

8.7 Renal Impairment

No dosage adjustment of BAXDELA is necessary in patients with mild (eGFR 60-89 mL/min/1.73 m^2) or moderate (eGFR 30-59 mL/min/1.73 m^2) renal impairment. The dose of BAXDELA intravenous IV infusion in patients with severe renal impairment (eGFR 15-29 mL/min/1.73 m^2) should be decreased to 200 mg intravenously every 12 hours; the dose of oral BAXDELA in patients with severe renal impairment (eGFR 15-29 mL/min/1.73 m^2) is 450 mg orally every 12 hours. BAXDELA is not recommended in patients with End Stage Renal Disease [ESRD] (eGFR of < 15 mL/min/1.73 m^2) [see Dosage and Administration (2.3) and Clinical Pharmacology (12.3)].

In patients with severe renal impairment or ESRD (eGFR of < 15 mL/min/1.73 m^2), accumulation of the intravenous vehicle, sulfobutylether-β-cyclodextrin (SBECD) occurs. Serum creatinine levels should be closely monitored in patients with severe renal impairment receiving intravenous BAXDELA. If serum creatinine level increases occur, consideration should be given to changing to oral BAXDELA. If eGFR decreases to < 15 mL/min/1.73 m^2, BAXDELA should be discontinued.

10 OVERDOSAGE

Treatment of overdose with BAXDELA should consist of observation and general supportive measures. Hemodialysis removed about 19% of delafloxacin and 56% of SBECD (Sulfobutylether β cyclodextrin) after intravenous administration of BAXDELA [see Clinical Pharmacology (12.3)].

11 DESCRIPTION

BAXDELA (delafloxacin) for Injection and BAXDELA (delafloxacin) Tablets contain meglumine salt of delafloxacin, a fluoroquinolone antibacterial. Delafloxacin meglumine is identified chemically as 1-Deoxy-1-(methylamino)-D-glucitol, 1-(6-amino-3,5-difluoropyridin-2-yl)-8-chloro-6-fluoro-7-(3-hydroxyazetidin-1-yl)-4-oxo-1,4-dihydroquinoline-3-carboxylate (salt), the chemical structure of which is shown below. The meglumine salt has a molecular weight of 635.97 g/mol, whereas the molecular weight of the delafloxacin free acid is 440.76 g/mol.

Figure 1 Chemical Structure

C18H12ClF3N4O4 ∙ C7H17NO5 M.W. 635.97

BAXDELA is intended for intravenous infusion or oral administration. BAXDELA is supplied as a sterile, lyophilized powder for injection and oral tablets as follows:

BAXDELA for Injection

Each vial of BAXDELA for Injection, 300 mg, is a sterile lyophilized powder that contains 300 mg delafloxacin (equivalent to 433 mg delafloxacin meglumine) and the following inactive ingredients: Edetate disodium (EDTA), (3.4 mg); meglumine (59 mg); sulfobutylether-β-cyclodextrin (2400 mg). Sodium hydroxide and/or hydrochloric acid may have been used to adjust the pH.

BAXDELA Tablets

Each BAXDELA tablet for oral use contains 450 mg delafloxacin (equivalent to 649 mg delafloxacin meglumine) and the following inactive ingredients: Citric acid anhydrous (5.5 mg); crospovidone (109 mg); magnesium stearate (10 mg); microcrystalline cellulose (417 mg); povidone (34 mg); sodium bicarbonate (140 mg); sodium phosphate monobasic monohydrate (5.5 mg).

12 CLINICAL PHARMACOLOGY

12.1 Mechanism of Action

BAXDELA is an antibacterial drug [see Microbiology (12.4)].

12.2 Pharmacodynamics

The antibacterial activity of delafloxacin appears to best correlate with the ratio of area under the concentration-time curve of free delafloxacin to minimal inhibitory concentration (fAUC/MIC) for Gram-positive organisms such as Staphylococcus aureus and Gram-negative organisms such as Escherichia coli based on animal models of infection.

Cardiac Electrophysiology

In a randomized, positive- and placebo-controlled, thorough QT/QTc study, 51 healthy subjects received BAXDELA 300 mg IV, BAXDELA 900 mg IV, oral moxifloxacin 400 mg, or placebo. Neither BAXDELA 300 mg nor BAXDELA 900 mg (three times the intravenous therapeutic dose) had any clinically relevant adverse effect on cardiac repolarization.

Photosensitivity Potential

A study of photosensitizing potential to ultraviolet (UVA and UVB) and visible radiation was conducted in 52 healthy volunteers (originally 13 subjects per treatment group). BAXDELA, at 200 mg/day and 400 mg/day (0.22 and 0.44 times the approved recommended daily oral dosage, respectively) for 7 days, and placebo did not demonstrate clinically significant phototoxic potential at any wavelengths tested (295 nm to 430 nm), including solar simulation. The active comparator (lomefloxacin) demonstrated a moderate degree of phototoxicity at UVA 335 nm and 365 nm and solar simulation wavelengths.

12.3 Pharmacokinetics

The pharmacokinetic parameters of delafloxacin following single- and multiple-dose (every 12 hours) oral (450 mg) and intravenous (300 mg) administration are shown in Table 6. Steady-state was achieved within approximately three days with accumulation of approximately 10% and 36% following IV and oral administration, respectively.

Table 6 Mean (SD) Delafloxacin Pharmacokinetic Parameters Following Single and Multiple Oral and Intravenous Administration
Parameters | Tablet |  | Intravenous Injection
Parameters | Single Dose 450 mg | Steady State 450 mg Q12h [Q12h is every 12 hours] | Single Dose 300 mg | Steady State 300 mg Q12h
Tmax (h) [Median (range)] | 0.75 (0.5, 4.0) | 1.00 (0.50, 6.00) | 1.0 (1.0, 1.2) | 1.0 (1.0, 1.0)
Cmax (µg/mL) | 7.17 (2.01) | 7.45 (3.16) | 8.94 (2.54) | 9.29 (1.83)
AUC (µg∙h/mL) [AUC is AUCτ (AUC from time 0 to 12 hours) for single dose and multiple-dose administration] | 22.7 (6.21) | 30.8 (11.4) | 21.8 (4.54) | 23.4 (6.90)
CL or CL/F(L/h) [CL is reported for intravenous injection. CL/F is reported for tablet] | 20.6 (6.07) | 16.8 (6.54) | 14.1 (2.81) | 13.8 (3.96)
CLr (L/h) | - | - | 5.89 (1.53) | 6.69 (2.19)
Rac | - | 1.36 | - | 1.1
Cmax = maximum concentration; Tmax = time to reach Cmax; AUC = area under the concentration-time curve; CL = systemic clearance; CL/F = apparent oral clearance; Rac = accumulation ratio

Absorption

The absolute bioavailability for BAXDELA 450 mg oral tablet administered as a single dose was 58.8%. The AUC of delafloxacin following administration of a single 450 mg oral (tablet) dose was comparable to that following a single 300 mg intravenous dose. The Cmax of delafloxacin was achieved within about 1 hour after oral administration under fasting condition. Food (kcal: 917, Fat: 58.5%, Protein: 15.4%, Carbohydrate: 26.2%). did not affect the bioavailability of delafloxacin [see Dosage and Administration (2.1)].

Distribution

The steady state volume of distribution of delafloxacin is 30–48 L which approximates total body water. The plasma protein binding of delafloxacin is approximately 84%; delafloxacin primarily binds to albumin. Plasma protein binding of delafloxacin is not significantly affected by renal impairment.

Following IV administration of 7 doses of 300 mg of BAXDELA to 30 healthy volunteers, the mean BAXDELA AUC0-12 (3.6 hr*mcg/mL) in alveolar macrophages was 80% of the free-plasma AUC0-12, and the mean BAXDELA AUC0-12 (2.8 hr*mcg/mL) in epithelial lining fluid was 70% of the free-plasma AUC0-12.

Elimination

In a mass balance study, the mean half-life for delafloxacin was 3.7 hours (SD 0.7 hour) after a single dose intravenous administration. The mean half-life values for delafloxacin ranged from 4.2 to 8.5 hours following multiple oral administrations. Following administration of a single 300 mg intravenous dose of BAXDELA, the mean clearance (CL) of delafloxacin was 16.3 L/h (SD 3.7 L/h), and the renal clearance (CLr) of delafloxacin accounts for 35-45% of the total clearance.

Metabolism

Glucuronidation of delafloxacin is the primary metabolic pathway with oxidative metabolism representing about 1% of an administered dose. The glucuronidation of delafloxacin is mediated mainly by UGT1A1, UGT1A3, and UGT2B15. Unchanged parent drug is the predominant component in plasma. There are no significant circulating metabolites in humans.

Excretion

After single intravenous dose of ^14C-labeled delafloxacin, 65% of the radioactivity was excreted in urine as unchanged delafloxacin and glucuronide metabolites and 28% was excreted in feces as unchanged delafloxacin. Following a single oral dose of ^14C-labeled delafloxacin, 50% of the radioactivity was excreted in urine as unchanged delafloxacin and glucuronide metabolites and 48% was excreted in feces as unchanged delafloxacin.

Specific Populations

No clinical significance in the pharmacokinetics of delafloxacin was observed based on age, sex, race, weight, body mass index, and disease state (ABSSSI and CABP).

Patients with Hepatic Impairment

No clinically meaningful changes in delafloxacin Cmax and AUC were observed, following administration of a single 300 mg intravenous dose of BAXDELA to patients with mild, moderate or severe hepatic impairment (Child-Pugh Class A, B, and C) compared to matched healthy control subjects.

Patients with Renal Impairment

Following a single intravenous (300 mg) administration of delafloxacin to subjects with mild (eGFR = 51-80 mL/min/1.73 m^2), moderate (eGFR = 31–50 mL/min/1.73 m^2), severe (eGFR = 15-29 mL/min/1.73 m^2) renal impairment, and ESRD on hemodialysis receiving intravenous delafloxacin within 1 hour before and 1 hour after hemodialysis, mean total exposure (AUCt) of delafloxacin was 1.3, 1.6, 1.8, 2.1, and 2.6-fold higher, respectively than that for matched normal control subjects. The mean dialysate clearance (CLd) of delafloxacin was 4.21 L/h (SD 1.56 L/h). After about 4 hours of hemodialysis, the mean fraction of administered delafloxacin recovered in the dialysate was about 19% [see Use in Specific Populations (8.7)].

Following a single oral (400 mg) administration of delafloxacin to subjects with mild (eGFR = 51-80 mL/min/1.73 m^2), moderate (eGFR = 31-50 mL/min/1.73 m^2), or severe (eGFR = 15-29 mL/min/1.73 m^2) renal impairment, the mean total exposure (AUCt) of delafloxacin was about 1.5-fold higher for subjects with moderate and severe renal impairment compared with healthy subjects, whereas total systemic exposures of delafloxacin in subjects with mild renal impairment were comparable with healthy subjects.

In patients with moderate (eGFR = 31–50 mL/min/1.73 m^2), or severe (eGFR = 15–29 mL/min/1.73 m^2) renal impairment or ESRD on hemodialysis, accumulation of the intravenous vehicle SBECD occurs. The mean systemic exposure (AUC) increased 2-fold, 5-fold, 7.5-fold, and 27-fold for patients with moderate impairment, severe impairment, ESRD on hemodialysis receiving intravenous delafloxacin within 1 hour before, and 1 hour after hemodialysis respectively, compared to the healthy control group. In subjects with ESRD undergoing hemodialysis, SBECD is dialyzed with a clearance of 4.74 L/h. When hemodialysis occurred 1 hour after the BAXDELA infusion in subjects with ESRD, the mean fraction of SBECD recovered in the dialysate was 56.1% over approximately 4 hours.

Geriatric Patients

Following single oral administration of 250 mg delafloxacin (approximately 0.6 times the approved recommended oral dose), the mean delafloxacin Cmax and AUC∞ values in elderly subjects (≥ 65 years) were about 35% higher compared to values obtained in young adults (18 to 40 years). This difference is not considered clinically relevant. A population pharmacokinetic analysis of patients with ABSSSI or CABP indicated that patients over the age of 65 years have slower clearance than younger patients. However, the overall impact on delafloxacin pharmacokinetics is not considered clinically significant and dose adjustment in elderly patients is not warranted.

Male and Female Patients

Following single oral administration of 250 mg delafloxacin (approximately 0.6 times the approved recommended oral dose), the mean delafloxacin Cmax and AUC∞ values in male subjects were comparable to female subjects. Results from a population pharmacokinetic analysis showed that females have a 24% lower AUC than males. This difference is not considered clinically relevant.

Drug Interaction Studies

Drug Metabolizing Enzymes

Delafloxacin at clinically relevant concentrations does not inhibit the cytochrome P450 isoforms CYP1A2, CYP2A6, CYP2B6, CYP2C8, CYP2C9, CYP2C19, CYP2D6, CYP2E1 and CYP3A4/5 in vitro in human liver microsomes. At a delafloxacin concentration (500 µM) well above clinically relevant exposures, the activity of CYP2E1was increased.

In human hepatocytes, delafloxacin showed no potential for in vitro induction of CYP1A2, 2B6, 2C19, or 2C8 but was a mild inducer of CYP2C9 at a concentration of 100 µM and CYP3A4 at a clinically relevant concentration. Administration of BAXDELA 450 mg every 12 hours for 5 days to healthy male and female subjects (n = 22) prior to and on Day 6 with a single oral 5 mg dose of midazolam (a sensitive CYP3A substrate), did not affect the Cmax and AUC values for midazolam or 1-hydroxy midazolam compared to administration of midazolam alone.

Transporters

Delafloxacin was not an inhibitor of the following hepatic and renal transporters in vitro at clinically relevant concentrations: MDR1, BCRP, OAT1, OAT3, OATP1B1, OATP1B3, BSEP, OCT1 and OCT2. Delafloxacin was not a substrate of OAT1, OAT3, OCT1, OCT2, OATP1B1 or OATP. Delafloxacin was shown to be a substrate of P-gp and BCRP in vitro. The clinical relevance of co-administration of delafloxacin and P-gp and/or BCRP inhibitors is unknown.

12.4 Microbiology

Mechanism of Action

Delafloxacin belongs to the fluoroquinolone class of antibacterial drugs and is anionic in nature. The antibacterial activity of delafloxacin is due to the inhibition of both bacterial topoisomerase IV and DNA gyrase (topoisomerase II) enzymes which are required for bacterial DNA replication, transcription, repair, and recombination. Delafloxacin exhibits a concentration-dependent bactericidal activity against gram-positive and gram-negative bacteria in vitro.

Resistance

Resistance to fluoroquinolones, including delafloxacin, can occur due to mutations in defined regions of the target bacterial enzymes topoisomerase IV and DNA gyrase referred to as Quinolone-Resistance Determining Regions (QRDRs), or through altered efflux.

Fluoroquinolones, including delafloxacin, have a different chemical structure and mechanism of action relative to other classes of antibacterial compounds (e.g., aminoglycosides, macrolides, β-lactams, glycopeptides, tetracyclines and oxazolidinones).

In vitro resistance to delafloxacin develops by multiple step mutations in the QRDRs of gram-positive and gram-negative bacteria. Delafloxacin-resistant mutants were selected in vitro at a frequency of < 10^-9.

Although cross-resistance between delafloxacin and other fluoroquinolone-class antibacterial agents has been observed, some isolates resistant to other fluoroquinolone-class antibacterial agents may be susceptible to BAXDELA including some S. aureus isolates carrying mutations in the quinolone resistance determining region (gyrA, parC and parE).

Additionally, delafloxacin has activity against some isolates of beta-lactamase positive H. influenzae and H. parainfluenzae.

Interaction With Other Antimicrobials

In vitro drug combination studies with delafloxacin and amoxicillin/clavulanate, azithromycin, aztreonam, ceftaroline, ceftazidime, ceftriaxone, colistin, daptomycin, doxycycline, linezolid, meropenem, penicillin, rifampin, tigecycline, trimethoprim/sulfamethoxazole and vancomycin demonstrated neither synergy nor antagonism.

Antimicrobial Activity

BAXDELA has been shown to be active against most isolates of the following microorganisms, both in vitro and in clinical infections, [see Indications and Usage (1.1, 1.2)].

Acute Bacterial Skin and Skin Structure Infections (ABSSSI)

Aerobic bacteria

Gram-positive bacteria
Staphylococcus aureus (including methicillin-resistant and methicillin-susceptible isolates)
Staphylococcus haemolyticus
Staphylococcus lugdunensis
Streptococcus pyogenes
Streptococcus agalactiae
Streptococcus anginosus Group (including S. anginosus, S. intermedius, and S. constellatus)
Enterococcus faecalis

Gram-negative bacteria
Escherichia coli
Klebsiella pneumoniae
Enterobacter cloacae
Pseudomonas aeruginosa

Community-Acquired Bacterial Pneumonia (CABP)

Aerobic bacteria

Gram-positive bacteria
Streptococcus pneumoniae
Staphylococcus aureus (methicillin-susceptible isolates only)

Gram-negative bacteria
Escherichia coli
Haemophilus influenzae
Haemophilus parainfluenzae
Klebsiella pneumoniae
Pseudomonas aeruginosa

Other microorganisms
Chlamydia pneumoniae
Legionella pneumophila
Mycoplasma pneumoniae

The following in vitro data are available, but their clinical significance is unknown. At least 90 percent of the following bacteria exhibit an in vitro minimum inhibitory concentration (MIC) less than or equal to the susceptible breakpoint of delafloxacin against isolates of similar genus or organism group. However, the efficacy of BAXDELA in treating clinical infections caused by these bacteria has not been established in adequate and well-controlled clinical trials.

Aerobic bacteria

Gram-positive bacteria
Streptococcus dysgalactiae

Gram-negative bacteria
Enterobacter aerogenes
Klebsiella oxytoca
Proteus mirabilis
Moraxella catarrhalis

Susceptibility Test Methods

For specific information regarding susceptibility test interpretive criteria and associated test methods and quality control standards recognized by FDA for this drug, please see: https://www.fda.gov/STIC.

13 NONCLINICAL TOXICOLOGY

13.1 Carcinogenesis, Mutagenesis, Impairment of Fertility

Long-term carcinogenicity studies have not been conducted with BAXDELA.

Delafloxacin was not mutagenic in a bacterial reverse mutation (Ames) assay, and was not clastogenic in a mouse bone marrow micronucleus test at ≥ 15 times the estimated human plasma exposure based on AUC. In an in vitro clastogenicity assay using isolated human lymphocytes, delafloxacin was negative in short incubations (~3 hours) and, at high cytotoxic concentrations (> 1.0 mM), was positive in a long incubation (~19 hours).

Delafloxacin did not affect the fertility of male and female rats up to the highest intravenous dose tested (120 mg/kg/day); female rats were dosed 2 weeks prior to mating and through gestation day 7 and male rats were treated for 28 days prior to mating and beyond for a total of 58-59 days. AUC in male and female (non-pregnant and pregnant) rats at 120 mg/kg/day delafloxacin intravenous was estimated to be approximately 5 times the estimated human plasma exposure based on AUC in separate intravenous toxicology studies in rats, one of which was a 2-week study that used a different vehicle for delafloxacin than in the fertility study, and another was an 8-day study in nonpregnant and pregnant (gestation day 13) rats that used the same vehicle for delafloxacin as in the fertility study.

13.2 Animal Toxicology and/or Pharmacology

Fluoroquinolone antibacterials are associated with degenerative changes in articular cartilage and arthropathy in skeletally immature animals. In a toxicology study of the formulated tablet in dogs, the femoral head of one of three high dose (480 mg/kg/day) females had minimal focal degeneration of the superficial articular cartilage and a small focal cleft in the articular cartilage. No other joints were examined.

14 CLINICAL STUDIES

14.1 Acute Bacterial Skin and Skin Structure Infections

A total of 1510 adults with acute bacterial skin and skin structure infections (ABSSSI) were randomized in 2 multicenter, multinational, double-blind, double-dummy, non-inferiority trials. Trial 1 compared BAXDELA 300 mg via intravenous infusion every 12 hours to comparator. In Trial 2, patients received BAXDELA 300 mg via intravenous infusion every 12 hours for 6 doses then made a mandatory switch to oral BAXDELA 450 mg every 12 hours. In both studies, the comparator was the intravenous combination of vancomycin 15 mg/kg actual body weight and aztreonam. Aztreonam therapy was discontinued if no gram-negative pathogens were identified in the baseline cultures.

In Trial 1, 331 patients with ABSSSI were randomized to BAXDELA and 329 patients were randomized to vancomycin plus aztreonam. Patients in this trial had the following infections: cellulitis (39%), wound infection (35%), major cutaneous abscess (25%), and burn infection (1%). The overall mean surface area of the infected lesion as measured by digital planimetry was 307 cm^2. The average age of patients was 46 years (range 18 to 94 years). Patients were predominately male (63%) and white (91%); 32% had BMI ≥ 30 kg/m^2. The population studied in Trial 1 included a distribution of patients with associated comorbidities such as hypertension (21%), diabetes (9%), and renal impairment (16%; 0.2% with severe renal impairment or ESRD). Current or recent history of drug abuse, including IV drug abuse, was reported by 55% of patients. Bacteremia was documented at baseline in 2% of patients.

In Trial 2, 423 patients were randomized to BAXDELA and 427 patients were randomized to vancomycin plus aztreonam. Patients in this trial had the following infections: cellulitis (48%), wound infection (26%), major cutaneous abscess (25%), and burn infection (1%). The overall mean surface area of the infected lesion, as measured by digital planimetry, was 353 cm^2. The average age of patients was 51 years (range 18 to 93 years). Patients were predominately male (63%) and white (83%); 50 % had a BMI ≥ 30 kg/m^2. The population studied in Trial 2 included a distribution of patients with associated comorbidities such as hypertension (31%), diabetes (13%) and renal impairment (16%; 0.2% with severe renal impairment or ESRD). Current or recent history of drug abuse, including IV drug abuse, was reported by 30% of patients. Bacteremia was documented at baseline in 2% of patients.

In both trials, objective clinical response at 48 to 72 hours post initiation of treatment was defined as a 20% or greater decrease in lesion size as determined by digital planimetry of the leading edge of erythema. Table 7 summarizes the objective clinical response rates in both of these trials.

Table 7 Clinical Response at 48–72 hours [Objective clinical response was defined as a 20% or greater decrease in lesion size as determined by digital planimetry of the leading edge of erythema at 48 to 72 hours after initiation of treatment without any reasons for failure (less than 20% reduction in lesion size, administration of rescue antibacterial therapy, use of another antibacterial or surgical procedure to treat for lack of efficacy, or death). Missing patients were treated as failures.] in the ITT Population with ABSSSI in Trial 1 and Trial 2
Trial | BAXDELA (300 mg IV) | Vancomycin 15 mg/kg + Aztreonam | Treatment Difference [Treatment difference, expressed as percentage, and CI based on Miettinen and Nurminen method without stratification.] (2-sided 95% CI)
Trial 1
Total N | 331 | 329
Responder, n (%) | 259 (78.2%) | 266 (80.9%) | -2.6 (-8.8, 3.6)
 | BAXDELA (300 mg IV and 450 mg oral) | Vancomycin 15 mg/kg + Aztreonam
Trial 2
Total N | 423 | 427
Responder, n (%) | 354 (83.7%) | 344 (80.6%) | 3.1 (-2.0, 8.3)
CI = Confidence Interval; ITT = Intent To Treat and includes all randomized patients

In both trials, an investigator assessment of response was made at Follow-up (Day 14 ± 1) in the ITT and CE populations. Success was defined as "cure + improved," where patients had complete or near resolution of signs and symptoms, with no further antibacterial needed. The success rates in the ITT and CE populations are shown in Table 8.

Table 8 Investigator-Assessed Success at the Follow-up Visit in ABSSSI —ITT Population and CE Population in Trial 1 and 2
Trial | BAXDELA (300 mg IV) | Vancomycin 15 mg/kg + Aztreonam | Treatment Difference [Treatment difference, expressed as percentage, and CI based on Miettinen and Nurminen method without stratification.] (2-sided 95% CI)
Trial 1
Success [Success was cure + improved where patients had complete or near resolution of signs and symptoms with no further antibacterial needed.] , n/N (%) ITT | 270/331 (81.6%) | 274/329 (83.3%) | -1.7 (-7.6, 4.1)
Success, n/N (%) CE | 232/240 (96.7%) | 238/244 (97.5%) | -0.9 (-4.3, 2.4)
 | BAXDELA (300 mg IV and 450 mg Oral) | Vancomycin 15 mg/kg + Aztreonam
Trial 2
Success, n/N (%) ITT | 369/423 (87.2%) | 362/427 (84.8%) | 2.5 (-2.2, 7.2)
Success, n/N (%) CE | 339/353 (96.0%) | 319/329 (97.0%) | -0.9 (-3.9, 2.0)
CI = Confidence Interval; ITT = Intent To Treat and includes all randomized patients; CE = Clinically Evaluable consisted of all ITT patients who had a diagnosis of ABSSSI, received at least 80% of expected doses of study drug, did not have any protocol deviations that would affect the assessment of efficacy and had investigator assessment at the Follow-Up Visit.

Six delafloxacin patients had baseline S. aureus bacteremia with ABSSSI. Five of these 6 patients (83.3%) were clinical responders at 48 to 72 hours and 5/6 (83.3%) were considered clinical success for ABSSSI at Day 14 ± 1. Two delafloxacin patients had baseline Gram-negative bacteremia (K. pneumoniae and P. aeruginosa), and both were clinical responders and successes.

The investigator assessments of clinical success rates were also similar between treatment groups at Late Follow-up (LFU, day 21-28).

Objective clinical response and investigator-assessed success by baseline pathogens from the primary infection site or blood cultures for the microbiological ITT (MITT) patient population pooled across Trial 1 and Trial 2 are presented in Table 9.

Table 9 Outcomes by Baseline Pathogen (Pooled across Trial 1 and Trial 2; MITT [Microbiological ITT (MITT) consists of all randomized patients who had a baseline pathogen identified that is known to cause ABSSSI.] Population)
 | Clinical Response [Objective clinical response was defined as a 20% or greater decrease in lesion size as determined by digital planimetry of the leading edge of erythema at 48 to 72 hours after initiation of treatment.] at 48–72 hours |  | Investigator-Assessed Success [Investigator-assessed success was defined as complete or near resolution of signs and symptoms, with no further antibacterial needed at Follow-up Visit (Day14 ± 1).] at Follow-up
 | BAXDELA | Comparator | BAXDELA | Comparator
Pathogen | n/N (%) | n/N (%) | n/N (%) | n/N (%)
Staphylococcus aureus | 271/319 (85.0) | 269/324 (83.0) | 275/319 (86.2) | 269/324 (83.0)
Methicillin-susceptible [Discrepancy in the total numbers is due to the multiple subjects having both MRSA and MSSA isolates.] | 149/177 (84.2) | 148/183 (80.9) | 154/177 (87.0) | 153/183 (83.6)
Methicillin-resistant | 125/144 (86.8) | 121/141 (85.8) | 122/144 (84.7) | 116/141 (82.3)
Streptococcus pyogenes | 17/23 (73.9) | 9/18 (50.0) | 21/23 (91.3) | 16/18 (88.9)
Staphylococcus haemolyticus | 11/15 (73.3) | 7/8 (87.5) | 13/15 (86.7) | 7/8 (87.5)
Streptococcus agalactiae | 10/14 (71.4) | 9/12 (75.0) | 12/14 (85.7) | 11/12 (91.7)
Streptococcus anginosus Group | 59/64 (92.2) | 55/61 (90.2) | 54/64 (84.4) | 47/61 (77.0)
Staphylococcus lugdunensis | 8/11 (72.7) | 6/9 (66.7) | 10/11 (90.9) | 8/9 (88.9)
Enterococcus faecalis | 11/11 (100.0) | 12/16 (75.0) | 9/11 (81.8) | 14/16 (87.5)
Escherichia coli | 12/14 (85.7) | 16/20 (80.0) | 12/14 (85.7) | 18/20 (90.0)
Enterobacter cloacae | 10/14 (71.4) | 8/11 (72.7) | 12/14 (85.7) | 10/11 (90.9)
Klebsiella pneumoniae | 19/22 (86.4) | 22/23 (95.7) | 20/22 (90.9) | 21/23 (91.3)
Pseudomonas aeruginosa | 9/11 (81.8) | 11/12 (91.7) | 11/11 (100.0) | 12/12 (100.0)

14.2 Community-Acquired Bacterial Pneumonia

A total of 859 adults with CABP were randomized in a multicenter, multinational, double-blind, double-dummy, noninferiority trial comparing BAXDELA to moxifloxacin (Trial 3, NCT 02679573). In this trial, BAXDELA for injection 300 mg was administered intravenously (IV) every 12 hours with an option to switch to BAXDELA tablet 450 mg orally every 12 hours. Moxifloxacin 400 mg was administered IV every 24 hours with an option to switch to moxifloxacin tablet 400 mg orally every 24 hours. Switch to oral treatment was allowed after a minimum of 3 days of IV dosing. Total treatment duration was 5 to 10 days. In the moxifloxacin arm, the investigator could switch patients to linezolid 600 mg every 12 hours if methicillin-resistant Staphylococcus aureus (MRSA) was confirmed.

A total of 431 patients were randomized to BAXDELA and 428 to moxifloxacin. Patient demographic and baseline characteristics were balanced between the treatment arms. In this trial, 12.9% of patients were in PORT Risk Class II, 60.3% were in PORT Risk Class III, 25.4% were in PORT Risk Class IV, and 1.4% were in PORT Risk Class V. The average age of patients was 60 years (range 18 to 93 years). Patients were predominantly male (58.7%) and white (91.5%); average BMI was 26.9 kg/m^2. Associated comorbidities included pre-existing pulmonary disease (13.6%), cardiac disease (23.9%), diabetes (15.3%), and mild to severe renal impairment (76.9%). Bacteremia was documented at baseline in 1.5% of patients. The majority of sites were in Eastern Europe, which accounted for 82.8% of enrollment. One subject (0.2%) was enrolled in the BAXDELA arm and 5 (1.2%) in the moxifloxacin arm from the United States.

Early clinical response (ECR) at 72-120 hours after the first dose was defined as survival with improvement in at least two of four symptoms (cough, sputum production, chest pain, dyspnea) from baseline without deterioration in any of these symptoms, and without use of additional antimicrobial therapy for treatment of the current CABP infection due to lack of efficacy.

Table 10 Early Clinical Response [Early Clinical Response (ECR) at 72-120 hours after the first dose, was defined as survival with improvement in at least two of four symptoms (cough, sputum production, chest pain, dyspnea) from baseline without deterioration in any of these symptoms, and without use of additional antimicrobial therapy for treatment of the current CABP infection due to lack of efficacy.] at 72 to 120 hours in the ITT Population with CABP (Trial 3)
Trial 3 | BAXDELA (300 mg IV and 450 mg oral) | Moxifloxacin (400 mg IV and 400 mg oral) | Treatment Difference [Treatment difference, expressed as percentage, and CI based on Miettinen and Nurminen method without stratification.] (2-sided 95% CI)
Total N | 431 | 428
Responder n (%) | 383 (88.9) | 381 (89.0) | -0.2 (-4.4, 4.1)
CI = Confidence Interval; ITT = Intent To Treat includes all randomized patients

Clinical response was also assessed by the investigator at the test of cure (TOC) visit and defined as survival with resolution or near resolution of the symptoms of CABP present at study entry, and no use of additional antimicrobial therapy for the current CABP infection, and no new symptoms associated with the current CABP infection.

Clinical response rates at the TOC visit for the ITT and Clinically Evaluable (CE) populations are presented in Table 11.

Table 11 Investigator-Assessed Success at the TOC Visit in CABP —ITT Population and CE Population in Trial 3
Trial 3 | BAXDELA (300 mg IV and 450 mg oral) | Moxifloxacin (400 mg IV and 400 mg oral) | Treatment Difference [Treatment difference, expressed as percentage, and CI based on Miettinen and Nurminen method without stratification.] (2-sided 95% CI)
Success [Success was survival with resolution or near resolution of the symptoms of CABP present at study entry, and no use of additional antimicrobial therapy for the current infection, and no new symptoms associated with the current CABP infection.] , n/N (%) ITT | 390/431 (90.5) | 384/428 (89.7) | 0.8 (-3.3, 4.8)
Success, n/N (%) CE | 376/397 (94.7) | 373/394 (94.7) | 0.0 (-3.2, 3.3)
CI = Confidence Interval; ITT = Intent To Treat and includes all randomized patients; CE = Clinically Evaluable
Clinically Evaluable consisted of all ITT patients who had evidence of acute CABP, received at least 80% of expected doses of the correct study drug, did not receive any concomitant, systemic antibacterial therapy except for lack of efficacy, and did not have any protocol deviations that would affect the assessment of efficacy.

Early clinical response and investigator-assessed clinical response at the TOC visit is presented in Table 12 by baseline pathogen for the Microbiological ITT (MITT) population which comprised all randomized patients who had a baseline pathogen identified that is known to cause CABP.

Table 12 Outcome by Baseline Pathogen (CABP, Trial 3, MITT Population) [Excludes patients with baseline pathogens resistant or non-susceptible to moxifloxacin.]
 | Early Clinical Response [Early Clinical Response (ECR) at 72-120 hours after the first dose, was defined as survival with improvement in at least two of four symptoms (cough, sputum production, chest pain, dyspnea) from baseline without deterioration in any of these symptoms, and without use of additional antimicrobial therapy for treatment of the current CABP infection due to lack of efficacy.] at 96 hours ± 24 hours |  | Investigator-Assessed Success [Investigator-assessed success was defined as survival with resolution or near resolution of the symptoms of CABP present at study entry, and no use of additional antimicrobial therapy for the current infection, and no new symptoms associated with the current CABP infection at Test of Cure (TOC) visit at (5 to 10 days after last dose of study drug).] at Test-of Cure (TOC)
 | BAXDELA | Moxifloxacin | BAXDELA | Moxifloxacin
Pathogen | n/N (%) | n/N (%) | n/N (%) | n/N (%)
Staphylococcus aureus | 24/26 (92.3) | 25/28 (89.3) | 24/26 (92.3) | 26/28 (92.9)
Methicillin-susceptible | 22/24 (91.7) | 25/28 (89.3) | 22/24 (91.7) | 26/28 (92.9)
Streptococcus pneumoniae | 66/71 (93.0) | 51/62 (82.3) | 64/71 (90.1) | 54/62 (87.1)
Haemophilus influenzae | 25/26 (96.2) | 31/35 (88.6) | 24/26 (92.3) | 31/35 (88.6)
Haemophilus parainfluenzae | 30/32 (93.8) | 27/33 (81.8) | 30/32 (93.8) | 26/33 (78.8)
Escherichia coli | 15/16 (93.8) | 8/11 (72.7) | 15/16 (93.8) | 10/11 (90.9)
Klebsiella pneumoniae | 13/17 (76.5) | 15/16 (93.8) | 14/17 (82.4) | 16/16 (100.0)
Pseudomonas aeruginosa | 12/13 (92.3) | 10/11 (90.9) | 11/13 (84.6) | 11/11 (100.0)
Chlamydia pneumoniae | 24/25 (96.0) | 14/16 (87.5) | 25/25 (100.0) | 16/16 (100.0)
Legionella pneumophilia | 27/29 (93.1) | 28/33 (84.8) | 27/29 (93.1) | 32/33 (97.0)
Mycoplasma pneumoniae | 30/35 (85.7) | 29/30 (96.7) | 34/35 (97.1) | 30/30 (100.0)

16 HOW SUPPLIED/STORAGE AND HANDLING

16.1 BAXDELA for Injection

BAXDELA is supplied as a sterile, lyophilized powder in single-dose clear glass vials of 300 mg delafloxacin (equivalent to 433 mg delafloxacin meglumine). The lyophilized powder is a light yellow to tan cake, which may exhibit cracking and shrinkage and slight variation in texture and color.

They are supplied as follows: 300 mg single-dose vials (NDC 70842-102-01), packaged in cartons of 10 vials (NDC 70842-102-03).

16.2 BAXDELA Tablets

BAXDELA Tablets contain 450 mg delafloxacin (equivalent to 649 mg delafloxacin meglumine); each modified capsule-shaped tablet in beige to mottled beige color is debossed with RX3341 on one side. They are supplied as follows:

Bottles of 20 tablets with child-resistant closure (NDC 70842-101-01)

Unit dose blister packs which contain 20 tablets (2 blister cards of 10 tablets each)
(20 tablet blister pack: NDC 70842-101-02, 10 tablet blister card: NDC 70842-101-03)

16.3 Storage and Handling

BAXDELA Tablets and BAXDELA for Injection should be stored at 20°C to 25°C (68°F to 77°F); excursions permitted to 15°C to 30°C (59°F to 86°F) [see USP Controlled Room Temperature].

The reconstituted powder may be stored for up to 24 hours under refrigerated or controlled room temperature and then further diluted for intravenous infusion. The reconstituted solution in the infusion bag may be stored under refrigerated or controlled room temperature conditions for up to 24 hours [see Dosage and Administration (2.4)]. Do not freeze.

17 PATIENT COUNSELING INFORMATION

Advise the patient to read the FDA-approved patient labeling (Medication Guide).

Serious Adverse Reactions

Advise patients to stop taking BAXDELA if they experience an adverse reaction and to call their healthcare provider for advice on completing the full course of treatment with another antibacterial drug.

Inform patients of the following serious adverse reactions that have been associated with BAXDELA or other fluoroquinolone use:

- Disabling and Potentially Irreversible Serious Adverse Reactions that may occur together: Inform patients that disabling and potentially irreversible serious adverse reactions, including tendinitis and tendon rupture, peripheral neuropathies, and central nervous system effects, have been associated with use of fluoroquinolones and may occur together in the same patient. Inform patients to stop taking BAXDELA immediately if they experience an adverse reaction and to call their healthcare provider.
- Tendinitis and Tendon Rupture: Instruct patients to contact their healthcare provider if they experience pain, swelling, or inflammation of a tendon, or weakness or inability to use one of their joints; rest and refrain from exercise; and discontinue BAXDELA treatment. Symptoms may be irreversible. The risk of severe tendon disorder with fluoroquinolones is higher in older patients usually over 60 years of age, in patients taking corticosteroid drugs, and in patients with kidney, heart or lung transplants.
- Peripheral Neuropathy: Inform patients that peripheral neuropathies have been associated with BAXDELA use, symptoms may occur soon after initiation of therapy and may be irreversible. If symptoms of peripheral neuropathy including pain, burning, tingling, numbness and/or weakness develop, immediately discontinue BAXDELA and tell them to contact their physician.
- Central Nervous System Effects: (for example, convulsions, dizziness, lightheadedness, increased intracranial pressure): Inform patients that convulsions have been reported in patients receiving fluoroquinolones. Instruct patients to notify their physician before taking this drug if they have a history of convulsions. Inform patients that they should know how they react to BAXDELA before they operate an automobile or machinery or engage in other activities requiring mental alertness and coordination. Instruct patients to notify their physician if persistent headache with or without blurred vision occurs.
- Exacerbation of Myasthenia Gravis: Instruct patients to inform their physician of any history of myasthenia gravis. Instruct patients to notify their physician if they experience any symptoms of muscle weakness, including respiratory difficulties.
- Hypersensitivity Reactions: Inform patients that BAXDELA can cause hypersensitivity reactions, even following a single dose, and to discontinue BAXDELA at the first sign of a skin rash, hives or other skin reactions, a rapid heartbeat, difficulty in swallowing or breathing, any swelling suggesting angioedema (for example, swelling of the lips, tongue, face, tightness of the throat, hoarseness), or other symptoms of an allergic reaction.
- Diarrhea: Diarrhea is a common problem caused by antibiotics which usually ends when the antibiotic is discontinued. Sometimes after starting treatment with antibiotics, patients can develop watery and bloody stools (with or without stomach cramps and fever) even as late as two or more months after having taken the last dose of the antibiotic. If this occurs, instruct patients to contact their physician as soon as possible.
- Aortic Aneurysm and Dissection: Inform patients to seek emergency medical care if they experience sudden chest, stomach, or back pain.
- Antibacterial Resistance: Patients should be counseled that antibacterial drugs including BAXDELA Tablets and Injection should only be used to treat bacterial infections. They do not treat viral infections (for example, the common cold). When BAXDELA Tablets and BAXDELA Injection are prescribed to treat a bacterial infection, patients should be told that although it is common to feel better early in the course of therapy, the medication should be taken exactly as directed. Skipping doses or not completing the full course of therapy may (1) decrease the effectiveness of the immediate treatment and (2) increase the likelihood that bacteria will develop resistance and will not be treatable by BAXDELA Tablets and BAXDELA Injection or other antibacterial drugs in the future.

Administration with Food and Concomitant Medications

- Inform patients that BAXDELA Tablets may be taken with or without food and without any dietary restrictions [see Dosage and Administration (2.1) and Clinical Pharmacology (12.3)].
- Inform patients that BAXDELA Tablets should be taken at least 2 hours before or 6 hours after antacids containing magnesium, or aluminum, with sucralfate, with metal cations such as iron, or with multivitamin preparations containing zinc or iron, or with didanosine buffered tablets for oral suspension or the pediatric powder for oral solution.

Distributed by:

Melinta Therapeutics, LLC
Lincolnshire, Illinois 60069 USA

Trademarks depicted herein are the property of their respective owners.

©2021 Melinta Therapeutics, LLC. All rights reserved.

MEL001-R007

MEDICATION GUIDE
BAXDELA® (Bax-de'-lah)
(delafloxacin) for injection

BAXDELA® (Bax-de'-lah)
(delafloxacin) tablets for oral use

What is the most important information I should know about BAXDELA?

BAXDELA, a fluoroquinolone antibacterial medicine, can cause serious side effects. Some of these serious side effects can happen at the same time and could result in death. If you get any of the following serious side effects while you take BAXDELA, you should stop taking BAXDELA immediately and get medical help right away.

1. Tendon rupture or swelling of the tendon (tendinitis).
  - Tendon problems can happen in people of all ages who take BAXDELA. Tendons are tough cords of tissue that connect muscles to bones. Symptoms of tendon problems may include:
    - Pain, swelling, tears and inflammation of tendons including the back of the ankle (Achilles), shoulder, hand, or other tendon sites.
  - The risk of getting tendon problems while you take BAXDELA is higher if you:
    - are over 60 years of age
    - are taking steroids (corticosteroids)
    - have had a kidney, heart or lung transplant
  - Tendon problems can happen in people who do not have the above risk factors when they take BAXDELA. Other reasons that can increase your risk of tendon problems can include:
    - physical activity or exercise
    - kidney failure
    - tendon problems in the past, such as in people with rheumatoid arthritis (RA)
  - Stop taking BAXDELA immediately and call your healthcare provider right away at the first sign of tendon pain, swelling or inflammation. Stop taking BAXDELA until tendinitis or tendon rupture has been ruled out by your healthcare provider. Avoid exercise and using the affected area. The most common area of pain and swelling is in the Achilles tendon at the back of your ankle. This can also happen with other tendons.
  - Talk to your healthcare provider about the risk of tendon rupture with continued use of BAXDELA. You may need a different antibacterial that is not a fluoroquinolone to treat your infection.
  - Tendon rupture can happen while you are taking or after you have finished taking fluoroquinolone antibacterial medicines like BAXDELA. Tendon ruptures can happen within hours or days of taking a fluoroquinolone and have happened up to several months after patients have finished taking their fluoroquinolone.
  - Stop taking BAXDELA immediately and get medical help right away if you get any of the following signs or symptoms of a tendon rupture:
    - hear or feel a snap or pop in a tendon area
    - bruising right after an injury in a tendon area
    - unable to move the affected area or bear weight
2. Changes in sensation and possible nerve damage (Peripheral Neuropathy). Damage to the nerves in arms, hands, legs, or feet can happen in people who take fluoroquinolones, including BAXDELA. Stop taking BAXDELA immediately and talk to your healthcare provider right away if you get any of the following symptoms of peripheral neuropathy in your arms, hands, legs, or feet:

- pain
- burning
- tingling

- numbness
- weakness

BAXDELA may need to be stopped to prevent permanent nerve damage.

3. Central Nervous System (CNS) effects. Seizures have been reported in people who take fluoroquinolone antibacterial medicines. Tell your healthcare provider if you have a history of seizures before you start taking BAXDELA. CNS side effects may happen as soon as after taking the first dose of BAXDELA. Stop taking BAXDELA immediately and talk to your healthcare provider right away if you get any of these side effects, or other changes in mood or behavior:

- seizures
- hear voices, see things, or sense things that are not there (hallucinations)
- feel restless
- tremors
- feel anxious or nervous
- confusion
- depression
- trouble sleeping
- nightmares

- feel lightheaded or dizzy
- feel more suspicious (paranoia)
- suicidal thoughts or acts
- headaches that will not go away, with or without blurred vision
- memory problems
- false or strange thoughts or beliefs (delusions)
- difficulty paying attention
- reduced awareness of surroundings

4. Worsening of Myasthenia Gravis (a problem that causes muscle weakness). Fluoroquinolones like BAXDELA may cause worsening of myasthenia gravis symptoms, including muscle weakness and breathing problems. Tell your healthcare provider if you have a history of myasthenia gravis before you start taking BAXDELA. Call your healthcare provider right away if you have any worsening muscle weakness or breathing problems.

What is BAXDELA?

BAXDELA is a fluoroquinolone antibacterial medicine used to treat certain types of infections caused by certain germs called bacteria in adults 18 years or older. These bacterial infections include:

- skin infections
- community-acquired bacterial pneumonia

It is not known if BAXDELA is safe and effective in people under 18 years of age, and use in people under 18 years of age is not recommended. Children younger than 18 years of age may have a higher chance of getting bone, joint, and tendon (musculoskeletal) problems while taking fluoroquinolone antibacterial medicines.

Sometimes infections are caused by viruses rather than by bacteria. Examples include viral infections in the sinuses and lungs, such as the common cold or flu. Antibacterial medicines, including BAXDELA, do not kill viruses. Call your healthcare provider if you think your condition is not getting better while you are taking BAXDELA.

Do not take BAXDELA if:

you have ever had a severe allergic reaction to an antibacterial known as a fluoroquinolone, or if you are allergic to any of the ingredients in BAXDELA. Ask your healthcare provider if you are not sure. See the list of ingredients in BAXDELA at the end of this Medication Guide.

What should I tell my healthcare provider before taking BAXDELA?

See "What is the most important information I should know about BAXDELA?"

Before you take BAXDELA, tell your healthcare provider about all your medical conditions, including if you:

- have tendon problems. BAXDELA should not be used in patients who have a history of tendon problems.
- have a disease that causes muscle weakness (myasthenia gravis). BAXDELA should not be used in patients who have a history of myasthenia gravis.
- have central nervous system problems (such as epilepsy).
- have nerve problems. BAXDELA should not be used in patients who have a history of a nerve problem called peripheral neuropathy.
- have a history of seizures.
- have kidney problems.
- have rheumatoid arthritis (RA) or other history of joint problems.
- have diabetes and take anti-diabetes medicines or insulin.
- are pregnant or planning to become pregnant. It is not known if BAXDELA will harm your unborn child.
- are breast-feeding or planning to breastfeed. It is not known if BAXDELA passes into human breast milk. You and your healthcare provider should decide whether you will take BAXDELA or breast-feed.

Tell your healthcare provider about all the medicines you take, including prescription and over-the-counter medicines, vitamins and herbal and dietary supplements.

BAXDELA and other medicines can affect each other causing side effects. Especially tell your healthcare provider if you take:

- A steroid medicine. Corticosteroids taken by mouth or by injection may increase the chance of tendon injury. See "What is the most important information I should know about BAXDELA?"
- Certain medicines may keep BAXDELA from working correctly. BAXDELA Tablets should be taken at least 2 hours before or 6 hours after:
  - an antacid, multivitamin, or other product that has magnesium, aluminum, iron, or zinc
  - sucralfate
  - didanosine buffered tablets for oral suspension or the pediatric powder for oral solution

Ask your healthcare provider if you are not sure if any of your medicines are listed above. Know the medicines you take. Keep a list of your medicines and show it to your healthcare provider and pharmacist when you get a new medicine.

How should I take BAXDELA?

- Take BAXDELA tablets 2 times a day exactly as your healthcare provider tells you to take it.
- If you have kidney problems, talk with your doctor about how you should take BAXDELA.
- BAXDELA can be taken with or without food.
- BAXDELA IV is given to you by intravenous (IV) infusion into your vein slowly, over 60 minutes, as prescribed by your healthcare provider.
- Do not skip any doses, or stop taking BAXDELA even if you begin to feel better, until you finish your prescribed treatment, unless you have:
  - tendon problems, nerve problems, or central nervous system problems (see "What is the most important information I should know about BAXDELA?").
  - a serious allergic reaction. See "What are the possible side effects of BAXDELA?"), or your healthcare provider tells you to stop.
  Unless you are experiencing any of the harmful side effects listed in this medication guide, take your BAXDELA, as your healthcare provider tells you to take it, to help lower the chance that bacteria will become resistant to BAXDELA. If this happens, BAXDELA and other antibacterial medicines may not work in the future.
- If you miss a dose of BAXDELA, take it as soon as you remember up to 8 hours before your next dose. If you have less than 8 hours before your next dose, wait to take your next dose at your regular time. Do not take more BAXDELA to make up for the missed dose.
- If you take too much BAXDELA, call your healthcare provider or get medical help immediately.

What should I avoid while taking BAXDELA?

BAXDELA can make you feel dizzy and lightheaded. Do not drive, operate machinery, or do other activities that require mental alertness or coordination until you know how BAXDELA affects you.

What are the possible side effects of BAXDELA?

BAXDELA may cause serious side effects, including:

- See "What is the most important information I should know about BAXDELA?"
- Serious allergic reactions. Serious allergic reactions, including death, can happen in people taking fluoroquinolones, including BAXDELA, even after only 1 dose. Stop taking BAXDELA and get emergency medical help right away if you get any of the following symptoms of a severe allergic reaction:

- hives
- swelling of the lips, tongue, face
- rapid heartbeat
- skin rash

- trouble breathing or swallowing
- throat tightness, hoarseness
- faint

Skin rash may happen in people taking fluoroquinolones even after only 1 dose. Stop taking BAXDELA at the first sign of a skin rash and call your healthcare provider. Skin rash may be a sign of a more serious reaction to BAXDELA.

- Clostridium difficile-associated diarrhea (CDAD). CDAD is an infection of your intestines (bowels) that can happen with many antibacterial medicines, including BAXDELA, and may cause mild diarrhea to life-threatening swelling of your intestines (colitis). Call your healthcare provider right away if you get stomach cramps, fever, watery diarrhea, diarrhea that does not go away, or bloody stools. CDAD can happen 2 or more months after you have finished your antibacterial medicine.
- Aortic aneurysm and dissection. Tell your healthcare provider if you have ever been told that you have an aortic aneurysm, a swelling of the large artery that carries blood from the heart to the body. Get emergency medical help right away if you have sudden chest, stomach or back pain.
- Changes in blood sugar. People who take fluoroquinolone medicines with oral anti-diabetes medicines or with insulin can get low blood sugar (hypoglycemia) and high blood sugar (hyperglycemia). Follow your healthcare provider's instructions for how often to check your blood sugar. If you have diabetes and you get low blood sugar while taking BAXDELA, stop taking BAXDELA and call your healthcare provider right away. Your antibiotic medicine may need to be changed.

The most common side effects of BAXDELA include:

- nausea
- diarrhea
- headache

- changes in liver tests
- vomiting

These are not all the possible side effects of BAXDELA. Call your doctor for medical advice about side effects. You may report side effects to FDA at 1-800-FDA-1088.

How should I store BAXDELA?

BAXDELA Tablets:

- Store BAXDELA Tablets at room temperature between 68°F to 77°F (20°C to 25°C).
- Keep BAXDELA away from moisture (humidity).

Keep BAXDELA and all medicines out of the reach of children.

General information about the safe and effective use of BAXDELA.

Medicines are sometimes prescribed for purposes other than those listed in a Medication Guide. Do not use BAXDELA for a condition for which it was not prescribed. Do not give BAXDELA to other people, even if they have the same symptoms that you have. It may harm them. You can ask your pharmacist or healthcare provider for information about BAXDELA that is written for health professionals.

What are the ingredients in BAXDELA?

- BAXDELA Tablets: 450 mg
  Active ingredient: 450 mg delafloxacin (equivalent to 649 mg delafloxacin meglumine)
  Inactive ingredients: Citric acid, Crospovidone, Magnesium stearate, Microcrystalline Cellulose, Povidone, Sodium bicarbonate, and Sodium phosphate monobasic, monohydrate.
- BAXDELA for Injection: 300 mg
  Active ingredient: delafloxacin
  Inactive ingredients: Meglumine, beta-cyclodextrin sulfobutyl ether, and EDTA. Sodium hydroxide and/or hydrochloric acid may have been used to adjust the pH.

Distributed by: Melinta Therapeutics, LLC
300 Tri-State International, Lincolnshire, Illinois, 60069 USA
Trademarks depicted herein are the property of their respective owners.
©2021 Melinta Therapeutics, LLC
All rights reserved
For more information go to BAXDELA.com or call 1-844-633-6568.

This Medication Guide has been approved by the U.S. Food and Drug Administration
MEL011-R007

Revised: 6/2021

PRINCIPAL DISPLAY PANEL - 450 mg Tablet Blister Pack Carton

NDC 70842-101-02

PHARMACIST: Please
dispense with medication
guide provided.

Baxdela®
(delafloxacin) tablets

450 mg per tablet

Contains 20 Tablets (2 blister cards of 10 tablets each)

Rx Only

Melinta
THERAPEUTICS

The
Antibiotics
Company

PRINCIPAL DISPLAY PANEL - 450 mg Tablet Bottle Carton

NDC 70842-101-01

Baxdela®
(delafloxacin) tablets

450 mg per tablet

Contains 20 Tablets
Rx Only

PHARMACIST: Please dispense
with medication guide provided.

melinta
therapeutics

PRINCIPAL DISPLAY PANEL - 20 Tablet Bottle Carton

NDC 70842-101-01

Baxdela®
(delafloxacin) tablets

450 mg per tablet

Contains 20 Tablets
Rx Only

PHARMACIST: Please dispense
with medication guide provided.

melinta
therapeutics

PRINCIPAL DISPLAY PANEL - 300 mg Vial Carton

NDC 70842-102-03

Baxdela®
(delafloxacin) for injection

300 mg per single-dose vial

Must be reconstituted and further diluted.
For intravenous infusion only.

Contains 10 Vials
Rx Only